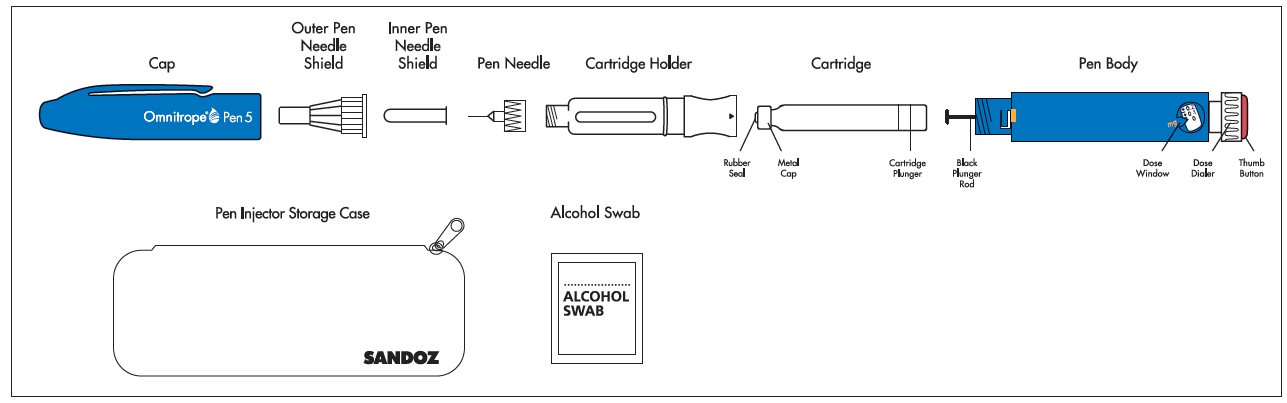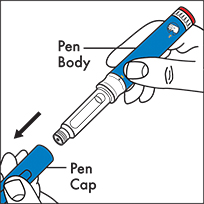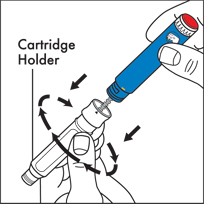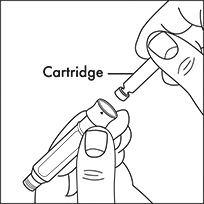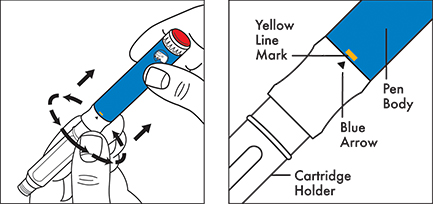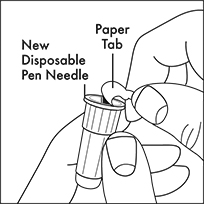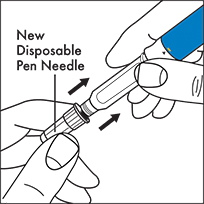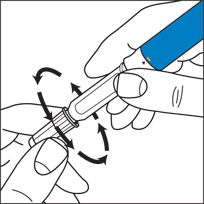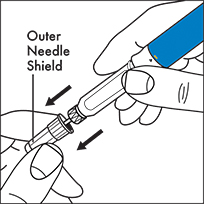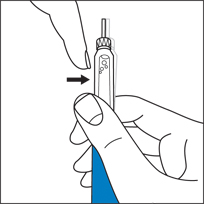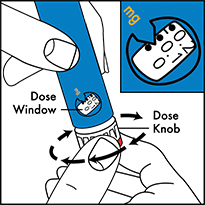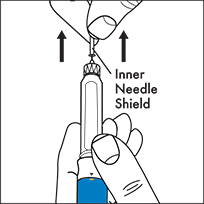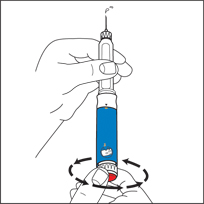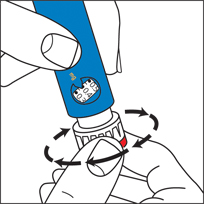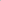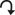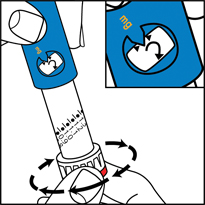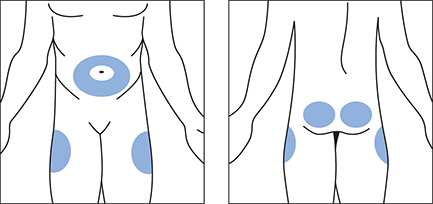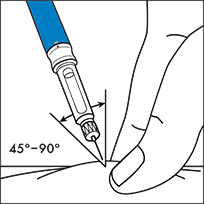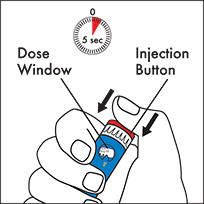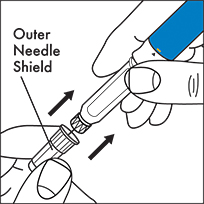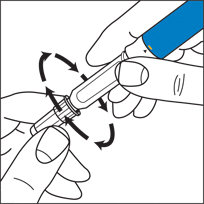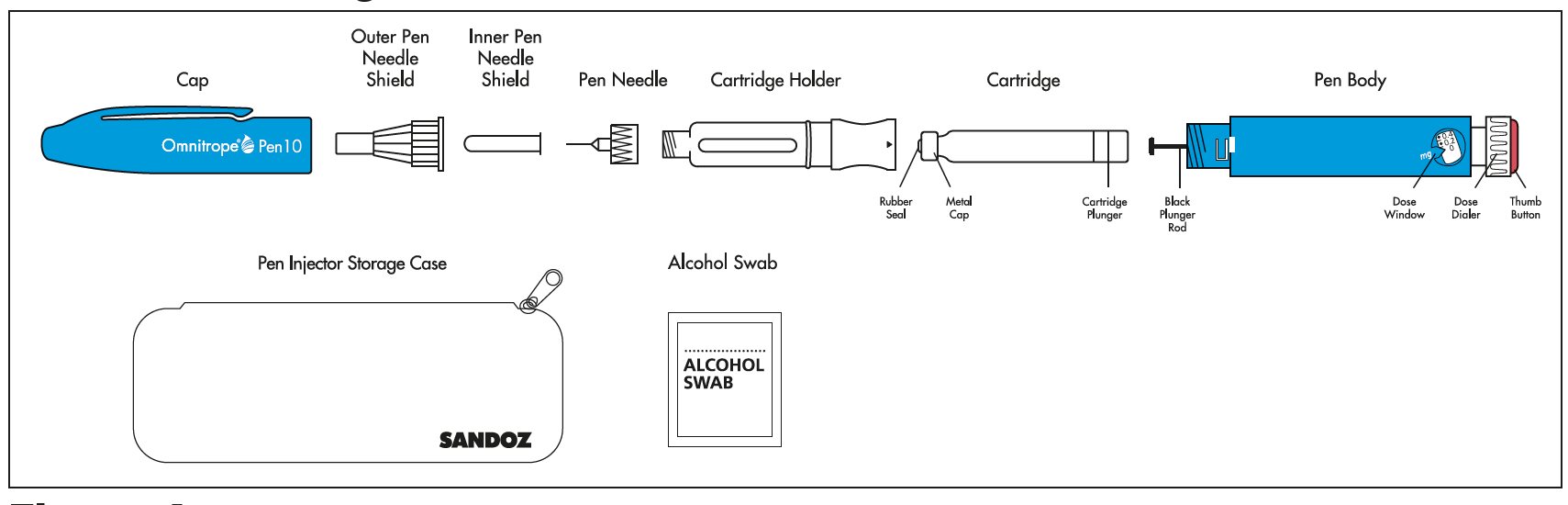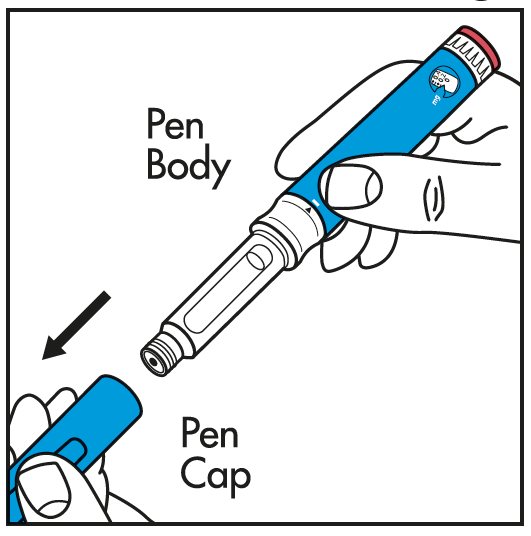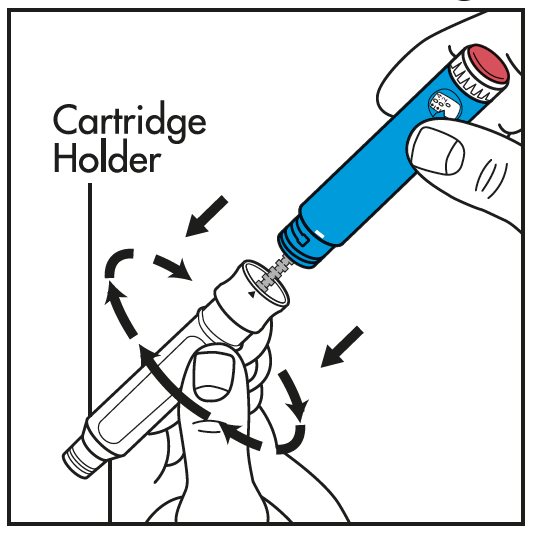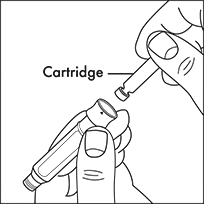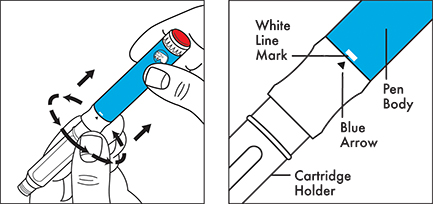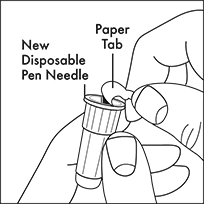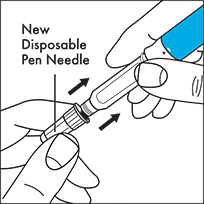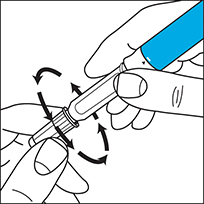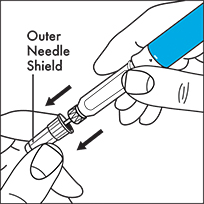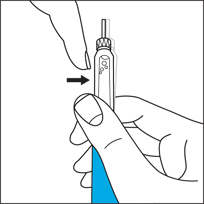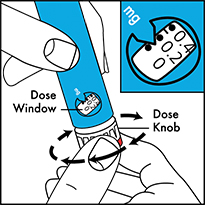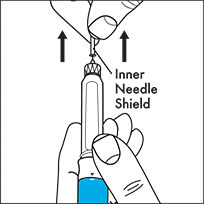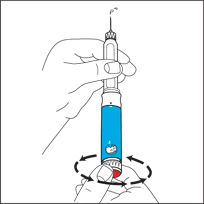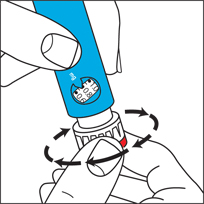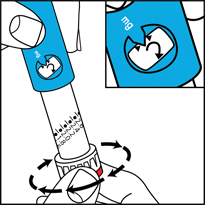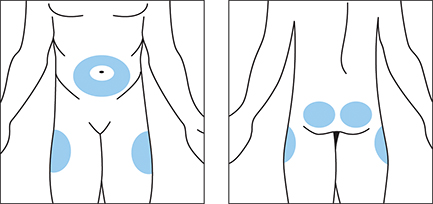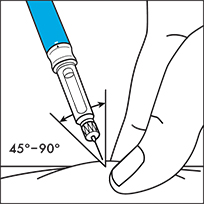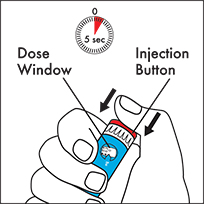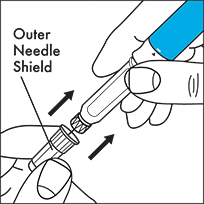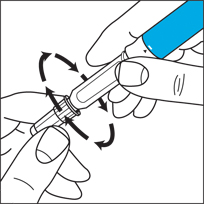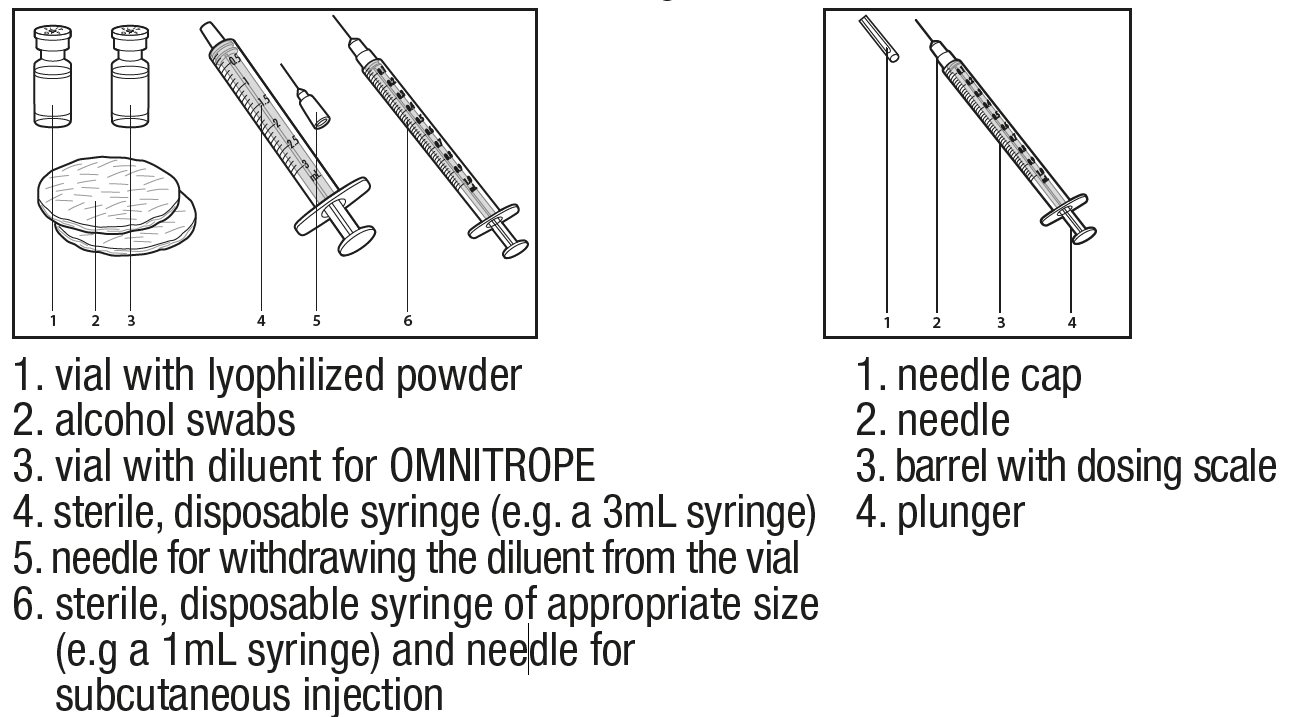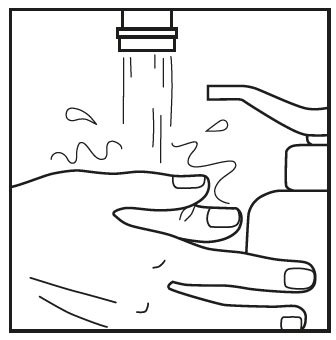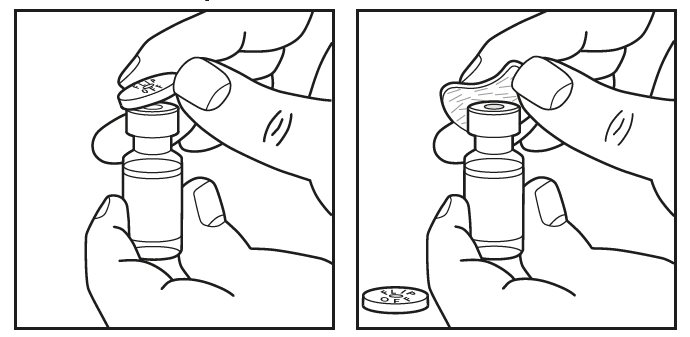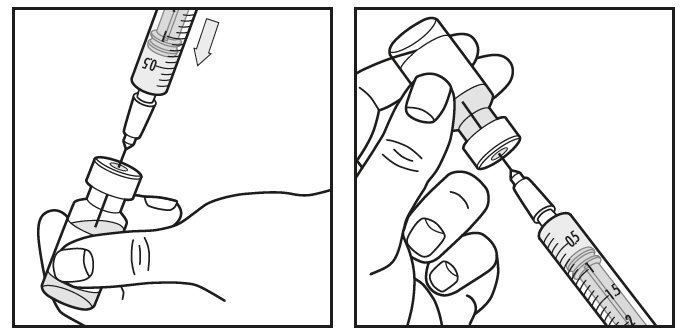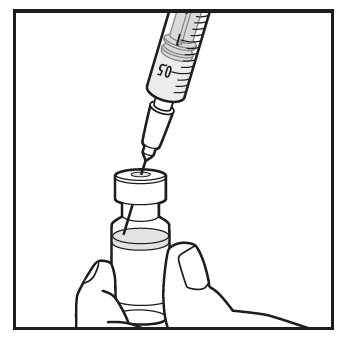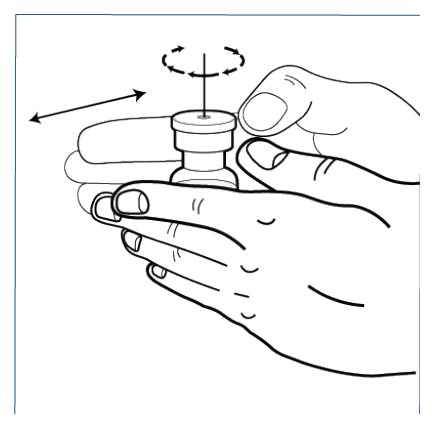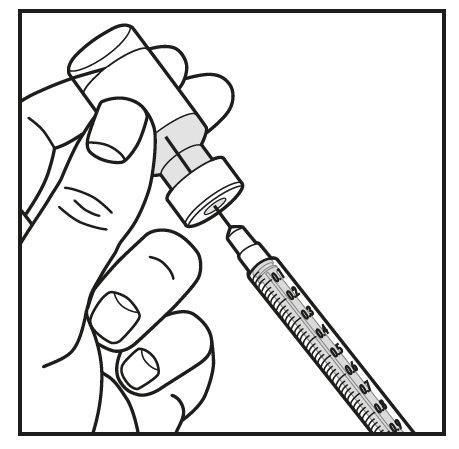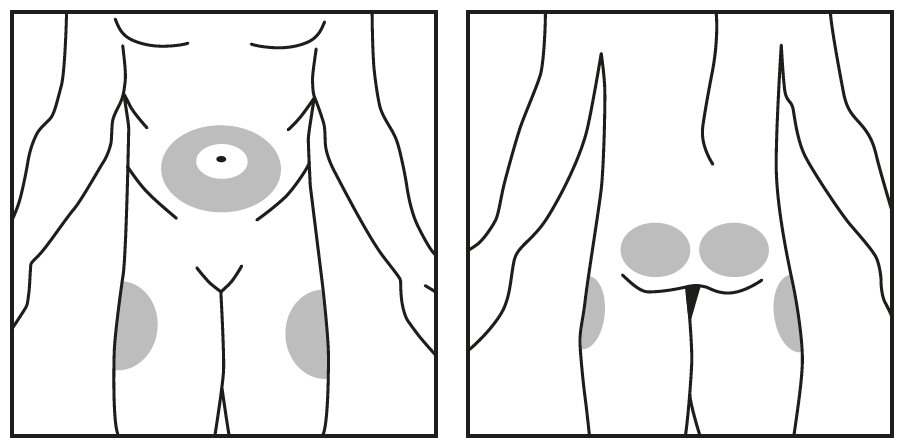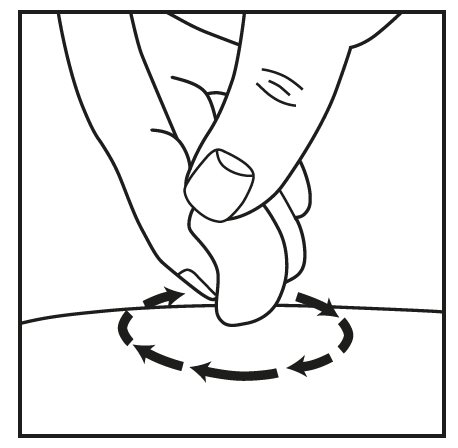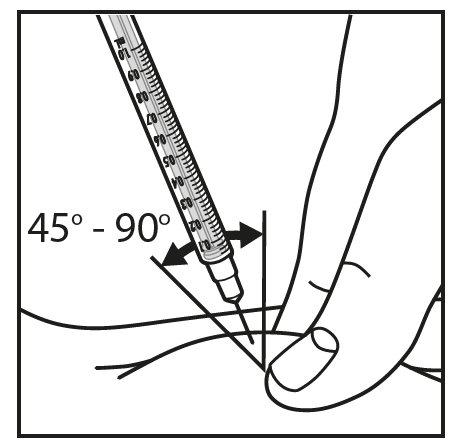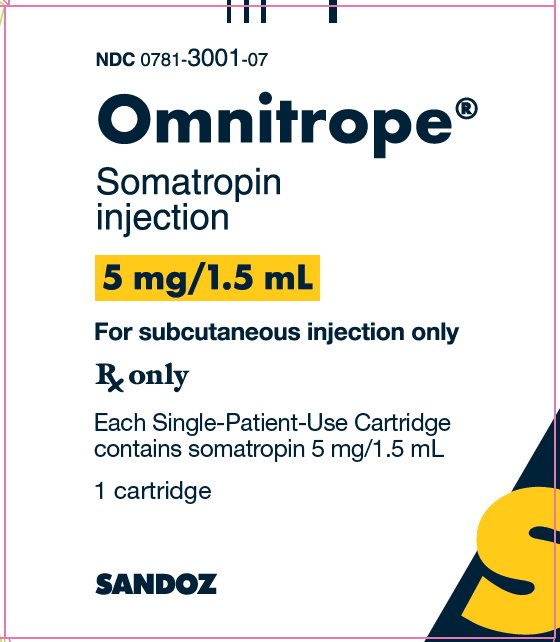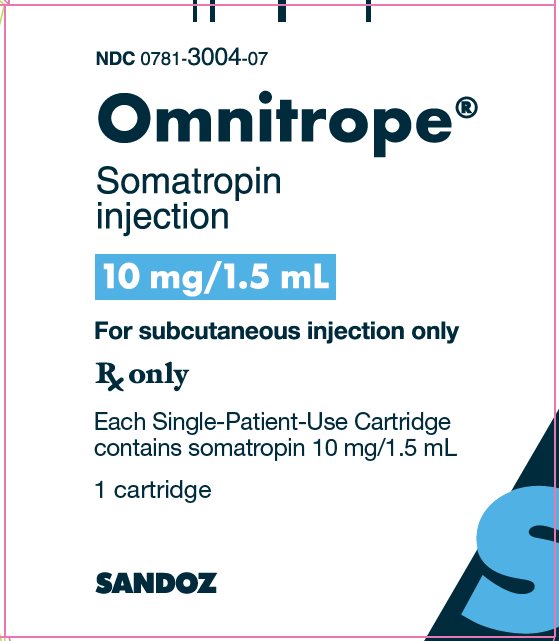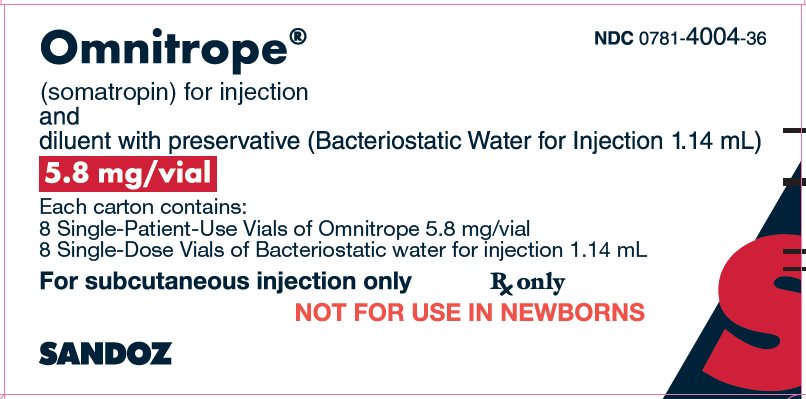 DRUG LABEL: Omnitrope
NDC: 0781-3001 | Form: INJECTION, SOLUTION
Manufacturer: Sandoz Inc
Category: prescription | Type: HUMAN PRESCRIPTION DRUG LABEL
Date: 20250710

ACTIVE INGREDIENTS: SOMATROPIN 5 mg/1.5 mL
INACTIVE INGREDIENTS: BENZYL ALCOHOL 13.5 mg/1.5 mL; MANNITOL 52.5 mg/1.5 mL; POLOXAMER 188 3 mg/1.5 mL; SODIUM PHOSPHATE, DIBASIC, ANHYDROUS 0.609 mg/1.5 mL; SODIUM PHOSPHATE, MONOBASIC, UNSPECIFIED FORM 1.28 mg/1.5 mL; WATER

HIGHLIGHTS OF PRESCRIBING INFORMATION

These highlights do not include all the information needed to use OMNITROPE safely and effectively. See full prescribing information for OMNITROPE.
OMNITROPE® (somatropin) injection, for subcutaneous use
OMNITROPE® (somatropin) for injection, for subcutaneous use
Initial U.S. Approval: 1987

RECENT MAJOR CHANGES

Warnings and Precautions, Slipped Capital Femoral Epiphysis in Pediatric Patients (5.10) 07/2025

1 INDICATIONS AND USAGE

OMNITROPE is a recombinant human growth hormone indicated for:

- Pediatric: Treatment of children with growth failure due to growth hormone deficiency (GHD), Prader-Willi Syndrome, Small for Gestational Age, Turner Syndrome, and Idiopathic Short Stature (1.1)
- Adult: Treatment of adults with either adult onset or childhood onset GHD (1.2)

2 DOSAGE AND ADMINISTRATION

OMNITROPE should be administered subcutaneously (2).

- Pediatric GHD: 0.16 to 0.24 mg/kg/week, divided into 6 to 7 daily injections (2.1)
- Prader-Willi Syndrome: 0.24 mg/kg/week, divided into 6 to 7 daily injections (2.1)
- Small for Gestational Age: Up to 0.48 mg/kg/week, divided into 6 to 7 daily injections (2.1)
- Turner Syndrome: 0.33 mg/kg/week, divided into 6 to 7 daily injections (2.1)
- Idiopathic Short Stature: Up to 0.47 mg/kg/week, divided into 6 to 7 daily injections (2.1)
- Adult GHD: not more than 0.04 mg/kg/week (divided into daily injections) to be increased as tolerated to not more than 0.08 mg/kg/week; to be increased gradually every 1 to 2 months (2.2)
- OMNITROPE Cartridges 5 mg/1.5 mL and 10 mg/1.5 mL must be used with the corresponding OMNITROPE Pen 5 and Pen 10 delivery system, respectively (2.3)
- Injection sites should always be rotated to avoid lipoatrophy (2.3)

3 DOSAGE FORMS AND STRENGTHS

- Injection: 5 mg/1.5 mL or 10 mg/1.5 mL solution in a single-patient-use prefilled cartridge (3)
- For injection: 5.8 mg lyophilized powder in a single-patient-use vial (3)

4 CONTRAINDICATIONS

- Acute Critical Illness (4)
- Children with Prader-Willi Syndrome who are severely obese or have severe respiratory impairment - reports of sudden death (4)
- Active Malignancy (4)
- Hypersensitivity to somatropin or its excipients (4)
- Active Proliferative or Severe Non-Proliferative Diabetic Retinopathy (4)
- Children with closed epiphyses (4)

5 WARNINGS AND PRECAUTIONS

- Acute Critical Illness: Potential benefit of treatment continuation should be weighed against the potential risk (5.1)
- Prader-Willi Syndrome in children: Evaluate for signs of upper airway obstruction and sleep apnea before initiation of treatment. Discontinue treatment if these signs occur (5.2)
- Neoplasm: Monitor patients with preexisting tumors for progression or recurrence. Increased risk of a second neoplasm in childhood cancer survivors treated with somatropin - in particular meningiomas in patients treated with radiation to the head for their first neoplasm (5.3)
- Impaired Glucose Tolerance and Diabetes Mellitus: May be unmasked. Periodically monitor glucose levels in all patients. Doses of concurrent antihyperglycemic drugs in diabetics may require adjustment (5.4)
- Intracranial Hypertension: Exclude preexisting papilledema. May develop and is usually reversible after discontinuation or dose reduction (5.5)
- Hypersensitivity: Serious hypersensitivity reactions may occur. In the event of an allergic reaction, seek prompt medical attention (5.6)
- Fluid Retention (i.e., edema, arthralgia, carpal tunnel syndrome - especially in adults): May occur frequently. Reduce dose as necessary (5.7)
- Hypoadrenalism: Monitor patients for reduced serum cortisol levels and/or need for glucocorticoid dose increases in those with known hypoadrenalism (5.8)
- Hypothyroidism: May first become evident or worsen (5.9)
- Slipped Capital Femoral Epiphysis: May develop. Evaluate children with the onset of a limp or hip/knee pain (5.10)
- Progression of Preexisting Scoliosis: May develop (5.11)
- Pancreatitis: Consider pancreatitis in patients with persistent severe abdominal pain (5.15)

6 ADVERSE REACTIONS

Other common somatropin-related adverse reactions include injection site reactions/rashes and lipoatrophy (6.1) and headaches (6.2).

To report SUSPECTED ADVERSE REACTIONS, contact Sandoz Inc. at 1-800-525-8747 or FDA at 1-800-FDA-1088 or http://www.fda.gov/medwatch

7 DRUG INTERACTIONS

- 11β-Hydroxysteroid Dehydrogenase Type 1: May require the initiation of glucocorticoid replacement therapy. Patients treated with glucocorticoid replacement for previously diagnosed hypoadrenalism may require an increase in their maintenance doses (7.1, 7.2)
- Pharmacologic Glucocorticoid Therapy and Supraphysiologic Glucocorticoid Treatment: Should be carefully adjusted (7.2)
- Cytochrome P450-Metabolized Drugs: Monitor carefully if used with somatropin (7.3)
- Oral Estrogen: Larger doses of somatropin may be required in women (7.4)
- Insulin and/or Oral Hypoglycemic Agents: May require adjustment (7.5)

FULL PRESCRIBING INFORMATION

1 INDICATIONS AND USAGE

1.1 Pediatric Patients

OMNITROPE is indicated for the treatment of children with growth failure due to inadequate secretion of endogenous growth hormone (GH).

OMNITROPE is indicated for the treatment of pediatric patients who have growth failure due to Prader-Willi Syndrome (PWS). The diagnosis of PWS should be confirmed by appropriate genetic testing [see Contraindications (4) and Warnings and Precautions (5.2)].

OMNITROPE is indicated for the treatment of growth failure in children born small for gestational age (SGA) who fail to manifest catch-up growth by age 2 years.

OMNITROPE is indicated for the treatment of growth failure associated with Turner Syndrome.

OMNITROPE is indicated for the treatment of idiopathic short stature (ISS), also called non-growth hormone-deficient short stature, defined by height standard deviation score (SDS) ≤ -2.25, and associated with growth rates unlikely to permit attainment of adult height in the normal range, in pediatric patients whose epiphyses are not closed and for whom diagnostic evaluation excludes other causes associated with short stature that should be observed or treated by other means.

1.2 Adult Patients

OMNITROPE is indicated for the replacement of endogenous GH in adults with growth hormone deficiency (GHD) who meet either of the following two criteria:

- Adult Onset (AO): Patients who have GHD, either alone or associated with multiple hormone deficiencies (hypopituitarism), as a result of pituitary disease, hypothalamic disease, surgery, radiation therapy, or trauma; or
- Childhood Onset (CO): Patients who were GH deficient during childhood as a result of congenital, genetic, acquired, or idiopathic causes.

Patients who were treated with somatropin for growth hormone deficiency in childhood and whose epiphyses are closed should be reevaluated before continuation of somatropin therapy at the reduced dose level recommended for growth hormone deficient adults. Confirmation of the diagnosis of adult growth hormone deficiency in both groups involves an appropriate growth hormone provocative test with two exceptions: (1) patients with multiple other pituitary hormone deficiencies due to organic disease; and (2) patients with congenital/genetic growth hormone deficiency.

2 DOSAGE AND ADMINISTRATION

The weekly dose should be divided over 6 or 7 days of subcutaneous injections.

Therapy with OMNITROPE should be supervised by a physician who is experienced in the diagnosis and management of pediatric patients with short stature associated with GHD, Prader-Willi Syndrome (PWS), Turner Syndrome (TS), those who were born small for gestational age (SGA), Idiopathic Short Stature (ISS) and adult patients with either childhood onset or adult onset GHD.

2.1 Dosing of Pediatric Patients

General Pediatric Dosing Information

The OMNITROPE dosage and administration schedule should be individualized based on the growth response of each patient.

Response to somatropin therapy in pediatric patients tends to decrease with time. However, in pediatric patients, the failure to increase growth rate, particularly during the first year of therapy, indicates the need for close assessment of compliance and evaluation for other causes of growth failure, such as hypothyroidism, undernutrition, advanced bone age and antibodies to recombinant human GH (rhGH).

Treatment with OMNITROPE for short stature should be discontinued when the epiphyses are fused.

Pediatric Growth Hormone Deficiency (GHD)

Generally, a dosage of 0.16 to 0.24 mg/kg body weight/week is recommended. The weekly dose should be divided over 6 or 7 days of subcutaneous injections.

Prader-Willi Syndrome (PWS)

Generally, a dosage of 0.24 mg/kg body weight/week is recommended. The weekly dose should be divided over 6 or 7 days of subcutaneous injections.

Small for Gestational Age (SGA)

Generally, a dosage of up to 0.48 mg/kg body weight/week is recommended. The weekly dose should be divided over 6 or 7 days of subcutaneous injections.

Turner Syndrome (TS)

Generally, a dose of 0.33 mg/kg body weight/week is recommended. The weekly dose should be divided over 6 or 7 days of subcutaneous injections.

Idiopathic Short Stature (ISS)

Generally, a dose up to 0.47 mg/kg of body weight/week is recommended. The weekly dose should be divided over 6 or 7 days of subcutaneous injections.

2.2 Dosing of Adult Patients

Adult Growth Hormone Deficiency (GHD)

Weight-Based Dosing

Based on the weight-based dosing utilized in clinical studies with another somatropin product, the recommended dosage at the start of therapy is not more than 0.04 mg/kg/week given as a daily subcutaneous injection. The dose may be increased at 4- to 8-week intervals according to individual patient requirements to not more than 0.08 mg/kg/week. Clinical response, side effects, and determination of age- and gender-adjusted serum IGF-1 levels may be used as guidance in dose titration.

Non-Weight Dosing

Alternatively, taking into account recent literature, a starting dose of approximately 0.2 mg/day (range, 0.15-0.30 mg/day) may be used without consideration of body weight. This dose can be increased gradually every 1-2 months by increments of approximately 0.1 to 0.2 mg/day, according to individual patient requirements based on the clinical response and serum IGF-1 concentrations. During therapy, the dose should be decreased if required by the occurrence of adverse events and/or serum IGF-1 levels above the age- and gender-specific normal range. Maintenance dosages vary considerably from person to person.

A lower starting dose and smaller dose increments should be considered for older patients, who are more prone to the adverse effects of somatropin than younger individuals. In addition, obese individuals are more likely to manifest adverse effects when treated with a weight-based regimen. In order to reach the defined treatment goal, estrogen-replete women may need higher doses than men. Oral estrogen administration may increase the dose requirements in women.

2.3 Preparation and Administration

OMNITROPE Cartridge 5 mg/1.5 mL and Cartridge 10 mg/1.5 mL

Each cartridge of OMNITROPE must be inserted into its corresponding OMNITROPE Pen 5 or OMNITROPE Pen 10 delivery system. Instructions for delivering the dosage are provided in the OMNITROPE INSTRUCTIONS FOR USE booklet enclosed with the OMNITROPE drug and the OMNITROPE Pens.

OMNITROPE for injection 5.8 mg/vial

Instructions for delivering the dosage are provided in the INSTRUCTIONS FOR USE leaflets enclosed with the OMNITROPE drug.

Once the diluent is added to the lyophilized powder, swirl gently; do not shake. Shaking may cause denaturation of the active ingredient.

Parenteral drug products should always be inspected visually for particulate matter and discoloration prior to administration, whenever solution and container permit. OMNITROPE MUST NOT BE INJECTED if the solution is cloudy or contains particulate matter. Use it only if it is clear and colorless. OMNITROPE must be refrigerated at 2° to 8°C (36° to 46°F).

Patients and caregivers who will administer OMNITROPE in medically unsupervised situations should receive appropriate training and instruction on the proper use of OMNITROPE from the physician or other suitably qualified health professional.

The dosage of OMNITROPE must be adjusted for the individual patient. The dose should be given daily by subcutaneous injections (administered preferably in the evening). OMNITROPE may be given in the thigh, buttocks, or abdomen.

Injection sites should always be rotated to avoid lipoatrophy.

3 DOSAGE FORMS AND STRENGTHS

Injection: 5 mg/1.5 mL or 10 mg/1.5 mL clear, colorless solution in a single-patient-use prefilled cartridge.

For Injection: 5.8 mg white to off-white lyophilized powder in a single-patient-use vial.

4 CONTRAINDICATIONS

OMNITROPE is contraindicated in patients with:
2. Acute Critical Illness

Treatment with pharmacologic amounts of somatropin is contraindicated in patients with acute critical illness due to complications following open heart surgery, abdominal surgery or multiple accidental trauma, or those with acute respiratory failure [see Warnings and Precautions (5.1)].

- Prader-Willi Syndrome in Children

Somatropin is contraindicated in patients with Prader-Willi Syndrome who are severely obese, have a history of upper airway obstruction or sleep apnea, or have severe respiratory impairment. There have been reports of sudden death when somatropin was used in such patients [see Warnings and Precautions (5.2)].

- Active Malignancy

In general, somatropin is contraindicated in the presence of active malignancy. Any preexisting malignancy should be inactive and its treatment complete prior to instituting therapy with somatropin. Somatropin should be discontinued if there is evidence of recurrent activity. Since GHD may be an early sign of the presence of a pituitary tumor (or, rarely, other brain tumors), the presence of such tumors should be ruled out prior to initiation of treatment. Somatropin should not be used in patients with any evidence of progression or recurrence of an underlying intracranial tumor [see Warnings and Precautions (5.3)].

- Hypersensitivity

OMNITROPE is contraindicated in patients with a known hypersensitivity to somatropin or any of its excipients. Systemic hypersensitivity reactions have been reported with postmarketing use of somatropins [see Warnings and Precautions (5.6)].

- Diabetic Retinopathy

Somatropin is contraindicated in patients with active proliferative or severe non-proliferative diabetic retinopathy.

- Closed Epiphyses

Somatropin should not be used for growth promotion in pediatric patients with closed epiphyses.

5 WARNINGS AND PRECAUTIONS

5.1 Acute Critical Illness

Increased mortality in patients with acute critical illness due to complications following open heart surgery, abdominal surgery or multiple accidental trauma, or those with acute respiratory failure has been reported after treatment with pharmacologic amounts of somatropin [see Contraindications (4)]. Two placebo-controlled clinical trials in non-growth hormone deficient adult patients (n=522) with these conditions in intensive care units revealed a significant increase in mortality (42% vs. 19%) among somatropin-treated patients (doses 5.3-8 mg/day) compared to those receiving placebo. The safety of continuing somatropin treatment in patients receiving replacement doses for approved indications who concurrently develop these illnesses has not been established. Therefore, the potential benefit of treatment continuation with somatropin in patients experiencing acute critical illnesses should be weighed against the potential risk.

5.2 Prader-Willi Syndrome in Children

There have been reports of fatalities after initiating therapy with somatropin in pediatric patients with Prader-Willi Syndrome who had one or more of the following risk factors: severe obesity, history of upper airway obstruction or sleep apnea, or unidentified respiratory infection. Male patients with one or more of these factors may be at greater risk than females. Patients with Prader-Willi Syndrome should be evaluated for signs of upper airway obstruction (including onset of or increased snoring) and sleep apnea before initiation of treatment with somatropin. If, during treatment with somatropin, patients show signs of upper airway obstruction (including onset of or increased snoring) and/or new onset sleep apnea, treatment should be interrupted. All patients with Prader-Willi Syndrome treated with somatropin should also have effective weight control and be monitored for signs of respiratory infection, which should be diagnosed as early as possible and treated aggressively [see Contraindications (4)].

5.3 Neoplasms

In childhood cancer survivors who were treated with radiation to the brain/head for their first neoplasm and who developed subsequent GHD and were treated with somatropin, an increased risk of a second neoplasm has been reported. Intracranial tumors, in particular meningiomas, were the most common of these second neoplasms. In adults, it is unknown whether there is any relationship between somatropin replacement therapy and CNS tumor recurrence [see Contraindications (4)]. Monitor all patients with a history of GHD secondary to an intracranial neoplasm routinely while on somatropin therapy for progression or recurrence of the tumor [see Contraindications (4)].

Because children with certain rare genetic causes of short stature have an increased risk of developing malignancies, practitioners should thoroughly consider the risks and benefits of starting somatropin in these patients. If treatment with somatropin is initiated, these patients should be carefully monitored for development of neoplasms.

Monitor patients on somatropin therapy carefully for increased growth, or potential malignant changes, of preexisting nevi.

5.4 Impaired Glucose Tolerance and Diabetes Mellitus

Treatment with somatropin may decrease insulin sensitivity, particularly at higher doses in susceptible patients. As a result, previously undiagnosed impaired glucose tolerance and overt diabetes mellitus may be unmasked, and new onset type 2 diabetes mellitus has been reported in patients taking somatropin. Therefore, glucose levels should be monitored periodically in all patients treated with somatropin, especially in those with risk factors for diabetes mellitus, such as obesity, Turner Syndrome, or a family history of diabetes mellitus. Patients with preexisting type 1 or type 2 diabetes mellitus or impaired glucose tolerance should be monitored closely during somatropin therapy. The doses of antihyperglycemic drugs (i.e., insulin or oral agents) may require adjustment when somatropin therapy is instituted in these patients [see Drug Interactions (7.5)].

5.5 Intracranial Hypertension (IH)

Intracranial hypertension (IH) with papilledema, visual changes, headache, nausea, and/or vomiting has been reported in a small number of patients treated with somatropins. Symptoms usually occurred within the first eight (8) weeks after the initiation of somatropin therapy. In all reported cases, IH-associated signs and symptoms rapidly resolved after cessation of therapy or a reduction of the somatropin dose.

Funduscopic examination should be performed routinely before initiating treatment with somatropin to exclude preexisting papilledema, and periodically during the course of somatropin therapy. If papilledema is observed by fundoscopy during somatropin treatment, treatment should be stopped. If somatropin-induced IH is diagnosed, treatment with somatropin can be restarted at a lower dose after IH-associated signs and symptoms have resolved. Patients with Turner Syndrome and Prader-Willi Syndrome may be at increased risk for the development of IH.

5.6 Hypersensitivity

Serious systemic hypersensitivity reactions including anaphylactic reactions and angioedema have been reported with postmarketing use of somatropins. Patients and caregivers should be informed that such reactions are possible and that prompt medical attention should be sought if an allergic reaction occurs [see Contraindications (4)].

5.7 Fluid Retention

Fluid retention during somatropin replacement therapy in adults may frequently occur. Clinical manifestations of fluid retention (e.g. edema, arthralgia, myalgia, nerve compression syndromes including carpal tunnel syndrome/paresthesias) are usually transient and dose dependent.

5.8 Hypoadrenalism

Patients receiving somatropin therapy who have or are at risk for pituitary hormone deficiency(s) may be at risk for reduced serum cortisol levels and/or unmasking of central (secondary) hypoadrenalism. In addition, patients treated with glucocorticoid replacement for previously diagnosed hypoadrenalism may require an increase in their maintenance or stress doses following initiation of somatropin treatment [see Drug Interactions (7.1)].

5.9 Hypothyroidism

Undiagnosed/untreated hypothyroidism may prevent an optimal response to somatropin, in particular, the growth response in children. Patients with Turner Syndrome have an inherently increased risk of developing autoimmune thyroid disease and primary hypothyroidism and should have their thyroid function checked prior to initiation of somatropin therapy. In patients with GHD, central (secondary) hypothyroidism may first become evident or worsen during somatropin treatment. Therefore, patients treated with somatropin should have periodic thyroid function tests and thyroid hormone replacement therapy should be initiated or appropriately adjusted when indicated.

5.10 Slipped Capital Femoral Epiphysis in Pediatric Patients

Slipped capital femoral epiphysis may occur more frequently in patients with endocrine disorders (including GHD and Turner Syndrome) or in patients undergoing rapid growth. Slipped capital femoral epiphysis may lead to osteonecrosis. Cases of slipped capital femoral epiphysis with or without osteonecrosis have been reported in pediatric patients with short stature receiving somatropin. Any pediatric patient with the onset of a limp or complaints of hip or knee pain during OMNITROPE therapy should be evaluated for slipped capital femoral epiphysis and osteonecrosis and managed accordingly.

5.11 Progression of Preexisting Scoliosis in Pediatric Patients

Progression of scoliosis can occur in patients who experience rapid growth. Because somatropin increases growth rate, patients with a history of scoliosis who are treated with somatropin should be monitored for progression of scoliosis. However, somatropin has not been shown to increase the occurrence of scoliosis. Skeletal abnormalities including scoliosis are commonly seen in untreated Turner Syndrome patients. Scoliosis is also commonly seen in untreated patients with Prader-Willi Syndrome. Physicians should be alert to these abnormalities, which may manifest during somatropin therapy.

5.12 Otitis Media and Cardiovascular Disorders in Turner Syndrome

Patients with Turner Syndrome should be evaluated carefully for otitis media and other ear disorders since these patients have an increased risk of ear and hearing disorders. Somatropin treatment may increase the occurrence of otitis media in patients with Turner Syndrome. In addition, patients with Turner Syndrome should be monitored closely for cardiovascular disorders (e.g., stroke, aortic aneurysm/dissection, hypertension) as these patients are also at risk for these conditions.

5.13 Lipoatrophy

When somatropin is administered subcutaneously at the same site over a long period of time, tissue atrophy may result. This can be avoided by rotating the injection site [see Dosage and Administration (2.3)].

5.14 Laboratory Tests

Serum levels of inorganic phosphorus, alkaline phosphatase, parathyroid hormone (PTH) and IGF-1 may increase after somatropin therapy.

5.15 Pancreatitis

Cases of pancreatitis have been reported rarely in children and adults receiving somatropin treatment, with some evidence supporting a greater risk in children compared with adults. Published literature indicates that girls who have Turner Syndrome may be at greater risk than other somatropin-treated children. Pancreatitis should be considered in any somatropin treated patient, especially a child, who develops persistent severe abdominal pain.

5.16 Benzyl Alcohol

Benzyl alcohol, a component of OMNITROPE Cartridge 5 mg/1.5 mL and the diluent for OMNITROPE for injection 5.8 mg/vial, has been associated with serious adverse events and death, particularly in pediatric patients. The “gasping syndrome,” (characterized by central nervous system depression, metabolic acidosis, gasping respirations, and high levels of benzyl alcohol and its metabolites found in the blood and urine) has been associated with benzyl alcohol dosages >99 mg/kg/day in neonates and low-birth weight neonates. Additional symptoms may include gradual neurological deterioration, seizures, intracranial hemorrhage, hematologic abnormalities, skin breakdown, hepatic and renal failure, hypotension, bradycardia, and cardiovascular collapse. Practitioners administering this and other medications containing benzyl alcohol should consider the combined daily metabolic load of benzyl alcohol from all sources.

6 ADVERSE REACTIONS

The following important adverse reactions are also described elsewhere in labeling:

- Increased mortality in patients with acute critical illness [see Warnings and Precautions (5.1)]
- Fatalities in children with Prader-Willi Syndrome [see Warnings and Precautions (5.2)]
- Neoplasms [see Warnings and Precautions (5.3)]
- Glucose intolerance and diabetes mellitus [see Warnings and Precautions (5.4)]
- Intracranial hypertension [see Warnings and Precautions (5.5)]
- Severe hypersensitivity [see Warnings and Precautions (5.6)]
- Fluid retention [see Warnings and Precautions (5.7)]
- Hypoadrenalism [see Warnings and Precautions (5.8)]
- Hypothyroidism [see Warnings and Precautions (5.9)]
- Slipped capital femoral epiphysis in pediatric patients [see Warnings and Precautions (5.10)]
- Progression of preexisting scoliosis in pediatric patients [see Warnings and Precautions (5.11)]
- Otitis media and cardiovascular disorders in patients with Turner Syndrome [see Warnings and Precautions (5.12)]
- Lipoatrophy [see Warnings and Precautions (5.13)]
- Pancreatitis [see Warnings and Precautions (5.15)]
- Benzyl Alcohol [see Warnings and Precautions (5.16)]

6.1 Clinical Trials Experience

Because clinical trials are conducted under varying conditions, adverse reaction rates observed during the clinical trials performed with one somatropin formulation cannot always be directly compared to the rates observed during the clinical trials performed with a second somatropin formulation, and may not reflect the adverse reaction rates observed in practice.

Clinical Trials in Pediatric GHD Patients

The following events were observed during clinical studies with OMNITROPE Cartridge conducted in children with GHD:

Table 1. Incidence of Adverse Reactions Reported in ≥ 5% Pediatric Patients with GHD During Treatment with OMNITROPE Cartridge (N=86)
Adverse Event | n (%)
Elevated HbA1c | 12 (14%)
Eosinophilia | 10 (12%)
Hematoma | 8 (9%)
N=number of patients receiving treatment
n=number of patients who reported the event during study period
%=percentage of patients who reported the event during study period

The following events were observed during clinical studies with OMNITROPE for injection conducted in children with GHD:

Table 2. Incidence of Adverse Reactions Reported in ≥ 5% Pediatric Patients with GHD During Treatment with OMNITROPE for Injection (N=44)
Adverse Event | n (%)
Hypothyroidism | 7 (16%)
Eosinophilia | 5 (11%)
Elevated HbA1c | 4 (9%)
Hematoma | 4 (9%)
Headache | 3 (7%)
Hypertriglyceridemia | 2 (5%)
Leg Pain | 2 (5%)
N=number of patients receiving treatment
n=number of patients who reported the event during study period
%= percentage of patients who reported the event during study period

Clinical Trials in PWS

In two clinical studies in pediatric patients with Prader-Willi Syndrome carried out with another somatropin product, the following drug-related events were reported: edema, aggressiveness, arthralgia, benign intracranial hypertension, hair loss, headache, and myalgia.

Clinical Trials in Children with SGA

In clinical studies of 273 pediatric patients born small for gestational age treated with another somatropin product, the following clinically significant events were reported: mild transient hyperglycemia, one patient with benign intracranial hypertension, two patients with central precocious puberty, two patients with jaw prominence, and several patients with aggravation of preexisting scoliosis, injection site reactions, and self-limited progression of pigmented nevi.

Clinical Trials in Children with Idiopathic Short Stature

In two open-label clinical studies conducted with another somatropin product in pediatric patients with ISS, the most commonly encountered adverse events were upper respiratory tract infections, influenza, tonsillitis, nasopharyngitis, gastroenteritis, headaches, increased appetite, pyrexia, fracture, altered mood, and arthralgia. In one of the two studies during treatment with this other somatropin product, the mean IGF-1 standard deviation (SD) scores were maintained in the normal range. IGF-1 SD scores above +2 SD were observed as follows: 1 subject (3%), 10 subjects (30%) and 16 subjects (38%) in the untreated control, 0.23 and the 0.47 mg/kg/week groups respectively, had at least one measurement; while 0 subjects (0%), 2 subjects (7%) and 6 subjects (14%) had two or more consecutive IGF-1 measurements above +2 SD.

Clinical Trials in Children with Turner Syndrome

In two clinical studies with another somatropin product in pediatric patients with Turner Syndrome, the most frequently reported adverse events were respiratory illnesses (influenza, tonsillitis, otitis, sinusitis), joint pain, and urinary tract infection. The only treatment-related adverse event that occurred in more than 1 patient was joint pain.

Clinical Trials in Adults with GHD

In clinical trials with another somatropin product in 1,145 GHD adults, the majority of the adverse events consisted of mild to moderate symptoms of fluid retention, including peripheral swelling, arthralgia, pain and stiffness of the extremities, peripheral edema, myalgia, paresthesia, and hypoesthesia. These events were reported early during therapy, and tended to be transient and/or responsive to dosage reduction.

Table 3 displays the adverse events reported by 5% or more of adult GHD patients in clinical trials after various durations of treatment with another somatropin product. Also presented are the corresponding incidence rates of these adverse events in placebo patients during the 6-month double-blind portion of the clinical trials.

Table 3. Adverse Events Reported by ≥ 5% of 1,145 Adult GHD Patients During Clinical Trials of Another Somatropin Product and Placebo, Grouped by Duration of Treatment
 | Double Blind Phase |  | Open Label Phase Another Somatropin Product
Adverse Event | Placebo 0–6 mo. (n = 572) % Patients | Another Somatropin Product 0–6 mo. (n = 573) % Patients | 6–12 mo. (n = 504) % Patients | 12–18 mo. (n = 63) % Patients | 18–24 mo. (n = 60) % Patients
Swelling, peripheral | 5.1 | 17.5 [Increased significantly when compared to placebo, P ≤ .025: Fisher’s Exact Test (one-sided)] | 5.6 | 0 | 1.7
Arthralgia | 4.2 | 17.3 | 6.9 | 6.3 | 3.3
Upper respiratory infection | 14.5 | 15.5 | 13.1 | 15.9 | 13.3
Pain, extremities | 5.9 | 14.7 | 6.7 | 1.6 | 3.3
Edema, peripheral | 2.6 | 10.8 | 3.0 | 0 | 0
Paresthesia | 1.9 | 9.6 | 2.2 | 3.2 | 0
Headache | 7.7 | 9.9 | 6.2 | 0 | 0
Stiffness of extremities | 1.6 | 7.9 | 2.4 | 1.6 | 0
Fatigue | 3.8 | 5.8 | 4.6 | 6.3 | 1.7
Myalgia | 1.6 | 4.9 | 2.0 | 4.8 | 6.7
Back pain | 4.4 | 2.8 | 3.4 | 4.8 | 5.0
n=number of patients receiving treatment during the indicated period
%=percentage of patients who reported the event during the indicated period

Post-Trial Extension Studies in Adults

In expanded post-trial extension studies, diabetes mellitus developed in 12 of 3,031 patients (0.4%) during treatment with another somatropin product. All 12 patients had predisposing factors, e.g., elevated glycated hemoglobin levels and/or marked obesity, prior to receiving this other somatropin product. Of the 3,031 patients receiving this other somatropin product, 61 (2%) developed symptoms of carpal tunnel syndrome, which lessened after dosage reduction or treatment interruption (52) or surgery (9). Other adverse events that have been reported include generalized edema and hypoesthesia.

6.2 Postmarketing Experience

The following adverse reactions have been identified during post approval use of somatropin or OMNITROPE. Because these adverse events are reported voluntarily from a population of uncertain size, it is not always possible to reliably estimate their frequency or establish a causal relationship to drug exposure. The adverse events reported during postmarketing surveillance do not differ from those listed/discussed above in Sections 6.1 and 6.2 in children and adults.

Serious systemic hypersensitivity reactions including anaphylactic reactions and angioedema have been reported with postmarketing use of somatropins [see Warnings and Precautions (5.6)].

Leukemia has been reported in a small number of GH deficient children treated with somatropin, somatrem (methionylated rhGH) and GH of pituitary origin. It is uncertain whether these cases of leukemia are related to GH therapy, the pathology of GHD itself, or other associated treatments such as radiation therapy. On the basis of current evidence, experts have not been able to conclude that GH therapy per se was responsible for these cases of leukemia. The risk for children with GHD, if any, remains to be established [see Contraindications (4) and Warnings and Precautions (5.3)].

The following additional adverse reactions have been observed during the use of somatropin: headaches (children and adults), gynecomastia (children), osteonecrosis (children), and pancreatitis (children and adults) [see Warnings and Precautions (5.16)].

New-onset type 2 diabetes mellitus has been reported.

7 DRUG INTERACTIONS

7.1 11β-Hydroxysteroid Dehydrogenase Type 1 (11βHSD-1)

The microsomal enzyme 11β-hydroxysteroid dehydrogenase type 1 (11βHSD-1) is required for conversion of cortisone to its active metabolite, cortisol, in hepatic and adipose tissue. GH and somatropin inhibit 11βHSD-1. Consequently, individuals with untreated GH deficiency have relative increases in 11βHSD-1 and serum cortisol. Introduction of somatropin treatment may result in inhibition of 11βHSD-1 and reduced serum cortisol concentrations. As a consequence, previously undiagnosed central (secondary) hypoadrenalism may be unmasked and glucocorticoid replacement may be required in patients treated with somatropin. In addition, patients treated with glucocorticoid replacement for previously diagnosed hypoadrenalism may require an increase in their maintenance or stress doses following initiation of somatropin treatment; this may be especially true for patients treated with cortisone acetate and prednisone since conversion of these drugs to their biologically active metabolites is dependent on the activity of 11βHSD-1 [see Warnings and Precautions (5.8)].

7.2 Pharmacologic Glucocorticoid Therapy and Supraphysiologic Glucocorticoid Treatment

Pharmacologic glucocorticoid therapy and supraphysiologic glucocorticoid treatment may attenuate the growth promoting effects of somatropin in children. Therefore, glucocorticoid replacement dosing should be carefully adjusted in children receiving concomitant somatropin and glucocorticoid treatments to avoid both hypoadrenalism and an inhibitory effect on growth.

7.3 Cytochrome P450-Metabolized Drugs

Limited published data indicate that somatropin treatment increases cytochrome P450 (CYP450)-mediated antipyrine clearance in man. These data suggest that somatropin administration may alter the clearance of compounds known to be metabolized by CYP450 liver enzymes (e.g., corticosteroids, sex steroids, anticonvulsants, cyclosporine). Careful monitoring is advisable when somatropin is administered in combination with other drugs known to be metabolized by CYP450 liver enzymes. However, formal drug interaction studies have not been conducted.

7.4 Oral Estrogen

In adult women on oral estrogen replacement, a larger dose of somatropin may be required to achieve the defined treatment goal [see Dosage and Administration (2.2)].

7.5 Insulin and/or Oral Hypoglycemic Agents

In patients with diabetes mellitus requiring drug therapy, the dose of insulin and/or oral agent may require adjustment when somatropin therapy is initiated [see Warnings and Precautions (5.4)].

8 USE IN SPECIFIC POPULATIONS

8.1 Pregnancy

Risk Summary

OMNITROPE contains the preservative benzyl alcohol. Because benzyl alcohol is rapidly metabolized by a pregnant woman, benzyl alcohol exposure in the fetus is unlikely. However, adverse reactions have occurred in premature neonates and low birth weight infants who received intravenously administered benzyl alcohol-containing drugs [see Warnings and Precautions (5.16)].

Limited available data with somatropin use in pregnant women are insufficient to determine a drug-associated risk of adverse developmental outcomes. In animal studies (rats and rabbits), there was no evidence of embryo‑fetal or neonatal harm following somatropin administration during organogenesis at doses approximately 24 times and 19 times the recommended human therapeutic levels, respectively, based on body surface area (see Data).

The estimated background risk of major birth defects and miscarriage for the indicated population is unknown. In the U.S. general population, the estimated background risks of major birth defects and miscarriage in clinically recognized pregnancies is 2% to 4% and 15% to 20%, respectively.

Data

Animal Data

Animal reproduction studies with somatropin during the period of organogenesis at doses of 0.3, 1, and 3.3 mg/kg/day administered subcutaneously in pregnant rats and 0.08, 0.3, and 1.3 mg/kg/day administered intramuscularly in pregnant rabbits were not teratogenic (highest doses approximately 24 times and 19 times the recommended human therapeutic levels, respectively, based on body surface area).

In perinatal and postnatal studies in rats, doses of 0.3, 1, and 3.3 mg/kg/day somatropin produced growth-promoting effects in the dams but not in the fetuses. Young rats at the highest dose showed increased weight gain during suckling but the effect was not apparent by 10 weeks of age. No adverse effects were observed on gestation, morphogenesis, parturition, lactation, postnatal development, or reproductive capacity of the offspring due to somatropin.

8.2 Lactation

Risk Summary

There is no information regarding the presence of somatropin in human milk. Limited published data indicate that exogenous somatropin does not increase normal breastmilk concentrations of growth hormone. No adverse effects related to somatropin in the breastfed infant have been reported. The developmental and health benefits of breastfeeding should be considered along with the mother's clinical need for OMNITROPE and any potential adverse effects on the breastfed infant from OMNITROPE or from the underlying maternal condition.

8.5 Geriatric Use

The safety and effectiveness of OMNITROPE in patients aged 65 and over have not been evaluated in clinical studies. Elderly patients may be more sensitive to the action of somatropin, and therefore may be more prone to develop adverse reactions. A lower starting dose and smaller dose increments should be considered for older patients [see Dosage and Administration (2.2)].

10 OVERDOSAGE

Short-Term

Short-term overdosage could lead initially to hypoglycemia and subsequently to hyperglycemia. Furthermore, overdose with somatropin is likely to cause fluid retention.

Long-Term

Long-term overdosage could result in signs and symptoms of gigantism and/or acromegaly consistent with the known effects of excess growth hormone [see Dosage and Administration (2)].

11 DESCRIPTION

Somatropin is a human growth hormone (GH) produced by recombinant DNA technology using Escherichia coli. The protein is comprised of 191 amino acid residues and a molecular weight of approximately 22,125 daltons. The amino acid sequence is identical to that of human GH of pituitary origin.

OMNITROPE (somatropin) injection is a clear, colorless, sterile solution for subcutaneous injection supplied in a cartridge for use with OMNITROPE Pen delivery system. Sodium hydroxide and/or phosphoric acid may be added during manufacture to adjust pH.

OMNITROPE (somatropin) for injection is a white to off-white lyophilized powder supplied in a vial for subcutaneous injection after reconstitution. Sodium hydroxide and/or hydrochloric acid may be added during manufacture to adjust pH. Vials are co-packaged with accompanying 1.14 mL vials of a diluent containing Bacteriostatic Water for Injection with 1.5% benzyl alcohol as a preservative. After reconstitution, the concentration is 5 mg/mL.

Each OMNITROPE cartridge or vial contains the following (see Table 4):

Table 4. Contents of OMNITROPE Cartridges and Vial
Product | Cartridge 5 mg/ 1.5 mL | Cartridge 10 mg/ 1.5 mL | For Injection 5.8 mg/ vial
Component
Somatropin | 5 mg | 10 mg | 5.8 mg
Dibasic sodium phosphate | 0.609 mg | 0.71 mg | 0.996 mg
Monobasic sodium phosphate | 1.28 mg | 1.2 mg | 0.52 mg
Poloxamer | 3 mg | 3 mg | -
Mannitol | 52.5 mg | - | -
Glycine | - | 27.75 mg | 27.6 mg
Benzyl alcohol | 13.5 mg | - | -
Phenol | - | 4.5 mg | -
Water for Injection | to make 1.5 mL | to make 1.5 mL | -
Diluent (vials only) |  |  | Bacteriostatic Water for Injection
Water for injection |  |  | to make 1.14 mL
Benzyl alcohol |  |  | 17 mg

12 CLINICAL PHARMACOLOGY

12.1 Mechanism of Action

Somatropin (as well as endogenous GH) binds to a dimeric GH receptor in the cell membrane of target cells resulting in intracellular signal transduction and a host of pharmacodynamic effects. Some of these pharmacodynamic effects are primarily mediated by IGF-1 produced in the liver and also locally (e.g., skeletal growth, protein synthesis), while others are primarily a consequence of the direct effects of somatropin (e.g., lipolysis) [see Pharmacodynamics (12.2)].

12.2 Pharmacodynamics

Tissue Growth

The primary and most intensively studied action of somatropin is the stimulation of linear growth. This effect is demonstrated in children with GHD and children who have PWS, were born SGA, have TS or have ISS.

Skeletal Growth

The measurable increase in bone length after administration of somatropin results from its effect on the cartilaginous growth areas of long bones. Studies in vitro have shown that the incorporation of sulfate into proteoglycans is not due to a direct effect of somatropin, but rather is mediated by the somatomedins or insulin-like growth factors (IGFs). The somatomedins, among them IGF-1, are polypeptide hormones which are synthesized in the liver, kidney, and various other tissues. IGF-1 levels are low in the serum of hypopituitary dwarfs and hypophysectomized humans or animals and increase after treatment with somatropin.

Cell Growth

It has been shown that the total number of skeletal muscle cells is markedly decreased in children with short stature lacking endogenous GH compared with normal children, and that treatment with somatropin results in an increase in both the number and size of muscle cells.

Organ Growth

Somatropin influences the size of internal organs, and it also increases red cell mass.

Protein Metabolism

Linear growth is facilitated in part by increased cellular protein synthesis. This synthesis and growth are reflected by nitrogen retention which can be quantitated by observing the decline in urinary nitrogen excretion and blood urea nitrogen following the initiation of somatropin therapy.

Carbohydrate Metabolism

Hypopituitary children sometimes experience fasting hypoglycemia that may be improved by treatment with somatropin. In healthy subjects, large doses of somatropin may impair glucose tolerance. Although the precise mechanism of the diabetogenic effect of somatropin is not known, it is attributed to blocking the action of insulin rather than blocking insulin secretion. Insulin levels in serum actually increase as somatropin levels increase. Administration of human growth hormone to normal adults and patients with growth hormone deficiency results in increases in mean serum fasting and postprandial insulin levels, although mean values remain in the normal range. In addition, mean fasting and postprandial glucose and hemoglobin A1C levels remain in the normal range.

Lipid Metabolism

Somatropin stimulates intracellular lipolysis, and administration of somatropin leads to an increase in plasma free fatty acids and triglycerides. Untreated GHD is associated with increased body fat stores, including increased abdominal visceral and subcutaneous adipose tissue. Treatment of growth hormone deficient patients with somatropin results in a general reduction of fat stores, and decreased serum levels of low density lipoprotein (LDL) cholesterol.

Mineral Metabolism

Administration of somatropin results in an increase in total body potassium and phosphorus and to a lesser extent sodium. This retention is thought to be the result of cell growth. Serum levels of phosphate increase in children with GHD after somatropin therapy due to metabolic activity associated with bone growth. Serum calcium levels are not altered. Although calcium excretion in the urine is increased, there is a simultaneous increase in calcium absorption from the intestine. Negative calcium balance, however, may occasionally occur during somatropin treatment.

Connective Tissue Metabolism

Somatropin stimulates the synthesis of chondroitin sulfate and collagen and increases the urinary excretion of hydroxyproline.

12.3 Pharmacokinetics

There are no pharmacokinetic studies using OMNITROPE Cartridges in patients with growth hormone deficiency.

Absorption

Following a subcutaneous injection of single dose of 5 mg OMNITROPE 5 mg/1.5 mL Cartridge or 5 mg OMNITROPE 10 mg/1.5 mL Cartridge in healthy male and female adults, the peak concentration (Cmax) was 72-74 mcg/L. The time to reach Cmax (tmax) for OMNITROPE was 4.0 hours.

The aqueous formulations of 5 mg/1.5 mL OMNITROPE cartridge and 10 mg/mL OMNITROPE cartridge are bioequivalent to the lyophilized 5.8 mg/vial OMNITROPE formulation.

Metabolism

Somatropin is metabolized in both the liver and kidneys by proteolytic degradation. In renal cells, at least a portion of the breakdown products are returned to the systemic circulation.

Excretion

The mean terminal half-life of somatropin after subcutaneous administration of OMNITROPE Cartridge in healthy adults is 2.5-2.8 hours. The mean clearance of subcutaneously administered OMNITROPE Cartridge in healthy adults was about 0.14 L/hr·kg.

Specific Populations

Pediatric: No pharmacokinetic studies of OMNITROPE have been conducted in pediatric patients.

Gender: The effect of gender on pharmacokinetics of OMNITROPE has not been evaluated in pediatric patients.

Race: No studies have been conducted with OMNITROPE to assess pharmacokinetic differences among races.

Renal or hepatic impairment: No pharmacokinetic studies have been conducted with OMNITROPE in patients with renal or hepatic impairment.

12.6 Immunogenicity

The observed incidence of anti-drug antibodies is highly dependent on the sensitivity and specificity of the assay. Differences in assay methods preclude meaningful comparisons of the incidence of anti-drug antibodies in the studies described below with the incidence of anti-drug antibodies in other studies, including those of OMNITROPE or other somatropins.

In the case of growth hormone, antibodies with binding capacities lower than 2 mg/mL have not been associated with growth attenuation. In a very small number of patients treated with somatropin, when binding capacity was greater than 2 mg/mL, interference with the growth response was observed.

13 NONCLINICAL TOXICOLOGY

13.1 Carcinogenesis, Mutagenesis, Impairment of Fertility

Carcinogenicity, mutagenicity, and fertility studies have not been conducted with OMNITROPE.

In rats receiving subcutaneous somatropin doses during gametogenesis and up to 7 days of pregnancy, 3.3 mg/kg/day (approximately 24 times human dose) produced anestrus or extended estrus cycles in females and fewer and less motile sperm in males. When given to pregnant female rats (days 1 to 7 of gestation) at 3.3 mg/kg/day a very slight increase in fetal deaths was observed. At 1 mg/kg/day (approximately seven times human dose) rats showed slightly extended estrus cycles, whereas at 0.3 mg/kg/day no effects were noted.

14 CLINICAL STUDIES

14.1 Pediatric Growth Hormone Deficiency (GHD)

The efficacy and safety of OMNITROPE were compared with another somatropin product approved for growth hormone deficiency (GHD) in pediatric patients. In sequential clinical trials involving a total of 89 GHD children, 44 patients received OMNITROPE for Injection (lyophilized powder) 5.8 mg/vial and 45 patients received the comparator somatropin product for 9 months. After 9 months of treatment patients who had received the comparator somatropin product were switched to OMNITROPE Cartridge (liquid) 5 mg/1.5 mL. After 15 months of treatment, all patients were switched to OMNITROPE Cartridge to collect long-term efficacy and safety data.

In both groups, somatropin was administered as a daily subcutaneous injection at a dose of 0.03 mg/kg. Similar effects on growth were observed between OMNITROPE for Injection and the comparator somatropin product during the initial 9 months of treatment.

The efficacy results after 9 months of treatment (OMNITROPE for Injection vs. the comparator somatropin product) and after 15 months (OMNITROPE Cartridge) are summarized in Table 5.

Table 5. Baseline Growth Characteristics and Effect of OMNITROPE after 9 and 15 Months of Treatment
Treatment Duration | Treatment Group | Treatment Group
0 - 9 months | OMNITROPE for Injection (n=44) | Another Somatropin Product; (n=45)
9 - 15 months | OMNITROPE for Injection (n=42) | OMNITROPE Cartridge (n=44)
Treatment Parameter | Mean (SD) | Mean (SD)
Height velocity (cm/yr)
Pre-treatment | 3.8 (1.2) | 4.0 (0.8)
Month 9 | 10.7 (2.6) | 10.7 (2.9)
Month 15 | 8.5 (1.8) | 8.6 (2.0)
Height velocity SDS
Pre-treatment | -2.4 (1.3) | -2.3 (1.1)
Month 9 | 6.1 (3.7) | 5.4 (3.2)
Month 15 | 3.4 (2.6) | 3.2 (2.9)
Height SDS
Pre-treatment | -3.0 (0.7) | -3.1 (0.9)
Month 9 | -2.3 (0.7) | -2.5 (0.7)
Month 15 | -2.0 (0.7) | -2.2 (0.7)
IGF-1 [Calculated only for patients with measurements above the level of detection]
Pre-treatment | 159 (92) | 158 (43)
Month 9 | 291 (174) | 302 (183)
Month 15 | 300 (225) | 323 (189)
IGFBP-3
Pre-treatment | 3.5 (1.3) | 3.5 (1.0)
Month 9 | 4.6 (3.0) | 4.0 (1.5)
Month 15 | 4.6 (1.3) | 4.9 (1.4)

14.2 Adult Growth Hormone Deficiency (GHD)

Another somatropin lyophilized powder was compared with placebo in six randomized clinical trials involving a total of 172 adult GHD patients. These trials included a 6-month double-blind treatment period, during which 85 patients received this other somatropin and 87 patients received placebo, followed by an open-label treatment period in which participating patients received this other somatropin for up to a total of 24 months. This other somatropin product was administered as a daily SC injection at a dose of 0.04 mg/kg/week for the first month of treatment and 0.08 mg/kg/week for subsequent months.

Beneficial changes in body composition were observed at the end of the 6-month treatment period for the patients receiving this other somatropin product as compared with the placebo patients. Lean body mass, total body water, and lean/fat ratio increased while total body fat mass and waist circumference decreased. These effects on body composition were maintained when treatment was continued beyond 6 months. Bone mineral density declined after 6 months of treatment but returned to baseline values after 12 months of treatment.

14.3 Prader-Willi Syndrome (PWS)

The safety and efficacy of another somatropin product in the treatment of pediatric patients with Prader-Willi Syndrome (PWS) were evaluated in two randomized, open-label, controlled clinical trials. Patients received either this other somatropin product or no treatment for the first year of the studies, while all patients received this other somatropin product during the second year. This other somatropin product was administered as a daily SC injection, and the dose was calculated for each patient every 3 months. In Study 1, the treatment group received this other somatropin product at a dose of 0.24 mg/kg/week during the entire study. During the second year, the control group received this other somatropin product at a dose of 0.48 mg/kg/week. In Study 2, the treatment group received this other somatropin product at a dose of 0.36 mg/kg/week during the entire study. During the second year, the control group received this other somatropin product at a dose of 0.36 mg/kg/week.

Patients who received this other somatropin product showed significant increases in linear growth during the first year of study, compared with patients who received no treatment (see Table 6). Linear growth continued to increase in the second year, when both groups received treatment with this other somatropin product.

Table 6. Efficacy of Another Somatropin Product in Pediatric Patients with Prader-Willi Syndrome (Mean ± SD)
 | Study 1 |  | Study 2
 | Another Somatropin Product (0.24 mg/kg/week) (n=15) | Untreated Control (n=12) | Another Somatropin Product (0.36 mg/kg/week) (n=7) | Untreated Control (n=9)
Linear growth (cm) Baseline height | 112.7 ± 14.9 | 109.5 ± 12.0 | 120.3 ± 17.5 | 120.5 ± 11.2
Growth from months 0 to 12 | 11.6 [p ≤ 0.001] ± 2.3 | 5.0 ± 1.2 | 10.7 ± 2.3 | 4.3 ± 1.5
Baseline SDS | -1.6 ± 1.3 | -1.8 ± 1.5 | -2.6 ± 1.7 | -2.1 ± 1.4
SDS at 12 months | -0.5 [p ≤ 0.002 (when comparing SDS change at 12 months)] ± 1.3 | -1.9 ± 1.4 | -1.4 ± 1.5 | -2.2 ± 1.4

Changes in body composition were also observed in the patients receiving this other somatropin product (see Table 7). These changes included a decrease in the amount of fat mass, and increases in the amount of lean body mass and the ratio of lean-to-fat tissue, while changes in body weight were similar to those seen in patients who received no treatment. Treatment with this other somatropin product did not accelerate bone age, compared with patients who received no treatment.

Table 7. Effect of Another Somatropin Product on Body Composition in Pediatric Patients with Prader-Willi Syndrome (Mean ± SD)
 | Another Somatropin Product (n=14) | Untreated Control (n=10)
Fat mass (kg) Baseline | 12.3 ± 6.8 | 9.4 ± 4.9
Change from months 0 to 12 | -0.9 [p < 0.005] ± 2.2 | 2.3 ± 2.4
Lean body mass (kg) Baseline | 15.6 ± 5.7 | 14.3 ± 4.0
Change from months 0 to 12 | 4.7 ± 1.9 | 0.7 ± 2.4
Lean body mass/Fat mass Baseline | 1.4 ± 0.4 | 1.8 ± 0.8
Change from months 0 to 12 | 1.0 ± 1.4 | -0.1 ± 0.6
Body weight (kg) [n=15 for the group receiving another somatropin product; n=12 for the Control group] Baseline | 27.2 ± 12.0 | 23.2 ± 7.0
Change from months 0 to 12 | 3.7 [n.s.] ± 2.0 | 3.5 ± 1.9

14.4 Pediatric Patients Born Small for Gestational Age (SGA) Who Fail to Manifest Catch-up Growth by Age 2

The safety and efficacy of another somatropin product in the treatment of children born small for gestational age (SGA) were evaluated in 4 randomized, open-label, controlled clinical trials. Patients (age range of 2 to 8 years) were observed for 12 months before being randomized to receive either this other somatropin product (two doses per study, most often 0.24 and 0.48 mg/kg/week) as a daily SC injection or no treatment for the first 24 months of the studies. After 24 months in the studies, all patients received this other somatropin product.

Patients who received any dose of this other somatropin product showed significant increases in growth during the first 24 months of study, compared with patients who received no treatment (see Table 8). Children receiving 0.48 mg/kg/week demonstrated a significant improvement in height standard deviation score (SDS) compared with children treated with 0.24 mg/kg/week. Both of these doses resulted in a slower but constant increase in growth between months 24 to 72 (data not shown).

Table 8. Efficacy of Another Somatropin Product in Children Born Small for Gestational Age (Mean ± SD)
 | Another Somatropin Product (0.24 mg/kg/week) (n=76) | Another Somatropin Product (0.48 mg/kg/week) (n=93) | Untreated Control (n=40)
Height Standard Deviation Score (SDS)
Baseline SDS | -3.2 ± 0.8 | -3.4 ± 1.0 | -3.1 ± 0.9
SDS at 24 months | -2.0 ± 0.8 | -1.7 ± 1.0 | -2.9 ± 0.9
Change in SDS from baseline to month 24 | 1.2 [p = 0.0001 vs Untreated Control group] ± 0.5 | 1.7, [p = 0.0001 vs group treated with another somatropin product 0.24 mg/kg/week] ± 0.6 | 0.1 ± 0.3

14.5 Idiopathic Short Stature (ISS)

The long-term efficacy and safety of another somatropin product in patients with idiopathic short stature (ISS) were evaluated in one randomized, open-label, clinical trial that enrolled 177 children. Patients were enrolled on the basis of short stature, stimulated GH secretion > 10 ng/mL, and prepubertal status (criteria for idiopathic short stature were retrospectively applied and included 126 patients). All patients were observed for height progression for 12 months and were subsequently randomized to this other somatropin product or observation only and followed to final height. Two somatropin doses were evaluated in this trial: 0.23 mg/kg/week (0.033 mg/kg/day) and 0.47mg/kg/week (0.067 mg/kg/day). Baseline patient characteristics for the ISS patients who remained prepubertal at randomization (n= 105) were: mean (± SD): chronological age 11.4 (1.3) years, height SDS -2.4 (0.4), height velocity SDS -1.1 (0.8), and height velocity 4.4 (0.9) cm/yr, IGF-1 SDS -0.8 (1.4). Patients were treated for a median duration of 5.7 years. Results for final height SDS are displayed by treatment arm in Table 9. Therapy with this other somatropin product improved final height in ISS children relative to untreated controls. The observed mean gain in final height was 9.8 cm for females and 5.0 cm for males for both doses combined compared to untreated control subjects. A height gain of 1 SDS was observed in 10% of untreated subjects, 50% of subjects receiving 0.23 mg/kg/week and 69% of subjects receiving 0.47 mg/kg/week.

Table 9. Final height SDS results for pre-pubertal patients with ISS [Mean (SD) are observed values.]
 | Untreated (n=30) | Another Somatropin Product 0.033 mg/kg/day (n=30) | Another Somatropin Product 0.067 mg/kg/day (n=42) | Another Somatropin Product 0.033 vs. Untreated (95% CI) | Another Somatropin Product 0.067 vs. Untreated (95% CI)
Baseline height SDS Final height SDS minus Baseline | 0.41 (0.58) | 0.95 (0.75) | 1.36 (0.64) | +0.53 (0.20, 0.87) p=0.0022 | +0.94 (0.63, 1.26) p<0.0001
Baseline predicted ht Final height SDS minus baseline predicted final height SDS | 0.23 (0.66) | 0.73 (0.63) | 1.05 (0.83) | +0.60 (0.09, 1.11) p=0.0217 | +0.90 (0.42, 1.39) p=0.0004
Least square means based on ANCOVA (final height SDS and final height SDS minus baseline predicted height SDS were adjusted for baseline height SDS)

14.6 Turner Syndrome

Two randomized, open-label, clinical trials were conducted that evaluated the efficacy and safety of another somatropin product in Turner Syndrome patients with short stature. Turner Syndrome patients were treated with this other somatropin product alone or this other somatropin product plus adjunctive hormonal therapy (ethinylestradiol or oxandrolone). A total of 38 patients were treated with this other somatropin product alone in the two studies. In Study 1, 22 patients were treated for 12 months, and in Study 2, 16 patients were treated for 12 months. Patients received this other somatropin product at a dose between 0.13 to 0.33 mg/kg/week.

SDS for height velocity and height are expressed using either the Tanner (Study 1) or Sempé (Study 2) standards for age-matched normal children as well as the Ranke standard (both studies) for age-matched, untreated Turner Syndrome patients. As seen in Table 10, height velocity SDS and height SDS values were smaller at baseline and after treatment with this other somatropin product when the normative standards were utilized as opposed to the Turner Syndrome standard.

Both studies demonstrated statistically significant increases from baseline in all of the linear growth variables (i.e., mean height velocity, height velocity SDS, and height SDS) after treatment with this other somatropin product (see Table 10). The linear growth response was greater in Study 1 wherein patients were treated with a larger dose of this other somatropin product.

Table 10. Growth Parameters (mean ± SD) after 12 Months of Treatment with Another Somatropin Product in Pediatric Patients with Turner Syndrome in Two Open Label Studies
 | Another somatropin product 0.33 mg/kg/week Study 1* n=22 | Another somatropin product 0.13-0.23 mg/kg/week Study 2† n=16
Height Velocity (cm/yr)
Baseline | 4.1 ± 1.5 | 3.9 ± 1.0
Month 12 | 7.8 ± 1.6 | 6.1 ± 0.9
Change from baseline (95% CI) | 3.7 (3.0, 4.3) | 2.2 (1.5, 2.9)
Height Velocity SDS (Tanner*/Sempé† Standards) (n=20)
Baseline | -2.3 ± 1.4 | -1.6 ± 0.6
Month 12 | 2.2 ± 2.3 | 0.7 ± 1.3
Change from baseline (95% CI) | 4.6 (3.5, 5.6) | 2.2 (1.4, 3.0)
Height Velocity SDS (Ranke Standard)
Baseline | -0.1 ± 1.2 | -0.4 ± 0.6
Month 12 | 4.2 ± 1.2 | 2.3 ± 1.2
Change from baseline (95% CI) | 4.3 (3.5, 5.0) | 2.7 (1.8, 3.5)
Height SDS (Tanner*/Sempé† Standards)
Baseline | -3.1 ± 1.0 | -3.2 ± 1.0
Month 12 | -2.7 ± 1.1 | -2.9 ± 1.0
Change from baseline (95% CI) | 0.4 (0.3, 0.6) | 0.3 (0.1, 0.4)
Height SDS (Ranke Standard)
Baseline | -0.2 ± 0.8 | -0.3 ± 0.8
Month 12 | 0.6 ± 0.9 | 0.1 ± 0.8
Change from baseline (95% CI) | 0.8 (0.7, 0.9) | 0.5 (0.4, 0.5)
SDS = Standard Deviation Score
Ranke standard based on age-matched, untreated Turner Syndrome patients
Tanner*/Sempé† standards based on age-matched normal children
p<0.05, for all changes from baseline

16 HOW SUPPLIED/STORAGE AND HANDLING

16.1 How Supplied

OMNITROPE (somatropin) injection is a clear, colorless, sterile solution for subcutaneous injection supplied in a cartridge for use with OMNITROPE Pen delivery system.

OMNITROPE (somatropin) for injection is a white to off-white lyophilized powder supplied in a vial for subcutaneous injection after reconstitution with co-packaged diluent.

Carton Contents | Strength | NDC
1 single-patient-use cartridge | 5 mg/1.5 mLa | NDC 0781-3001-07
5 single-patient-use cartridges | 5 mg/1.5 mLa | NDC 0781-3001-26
1 single-patient-use cartridge | 10 mg/1.5 mLb | NDC 0781-3004-07
5 single-patient-use cartridges | 10 mg/1.5 mLb | NDC 0781-3004-26
8 single-patient-use vials; 8 single-dose vials of diluent (Bacteriostatic Water for Injection containing 1.5% benzyl alcohol as a preservative) | 5.8 mg per vial | NDC 0781-4004-36

a For use only with the OMNITROPE Pen 5 delivery system, which is sold separately.

b For use only with the OMNITROPE Pen 10 delivery system, which is sold separately.

16.2 Storage and Handling

Before use, store OMNITROPE vials and cartridges refrigerated at 2° to 8°C (36° to 46°F) in the original carton to protect from light. Do not freeze.

After first use, the OMNITROPE cartridge should remain in the pen and kept the original carton in a refrigerator at 2° to 8°C (36° to 46°F) for a maximum of 28 days (see Table 11). Discard unused portions in the cartridge after 28 days.

After reconstitution of the lyophilized powder, the contents of the OMNITROPE vial must be used within 21 days. After the first injection, store the vial in the original carton in a refrigerator at 2° to 8°C (36° to 46°F) (see Table 11). Discard unused portions after 21 days.

Table 11. Storage Options
OMNITROPE Product Formulation | Storage Requirement
OMNITROPE Product Formulation | Before Use | In-use (after 1st injection)
5 mg/1.5 mL cartridge | Refrigerate at; 2° to 8°C (36° to 46°F) Until exp date | Refrigerate at; 2° to 8°C (36° to 46°F) up to 28 days
10 mg/1.5 mL cartridge | Refrigerate at; 2° to 8°C (36° to 46°F) Until exp date | Refrigerate at; 2° to 8°C (36° to 46°F) up to 28 days
5.8 mg per vial | Refrigerate at; 2° to 8°C (36° to 46°F) Until exp date | Refrigerate at; 2° to 8°C (36° to 46°F) up to 21 days

17 PATIENT COUNSELING INFORMATION

See FDA-approved patient labeling (Instructions For Use: OMNITROPE Pen 5 Instructions For Use, OMNITROPE Pen 10 Instructions For Use, Instructions For OMNITROPE 5.8 mg/Vial).

Patients being treated with OMNITROPE (and/or their parents) should be informed about the potential risks and benefits associated with somatropin treatment. This information is intended to better educate patients (and caregivers); it is not a disclosure of all possible adverse or intended effects.

Patients and caregivers who will administer OMNITROPE should receive appropriate training and instruction on the proper use of OMNITROPE from the physician or other suitably qualified health care professional. A puncture-resistant container for the disposal of used syringes and needles should be strongly recommended. Patients and/or parents should be thoroughly instructed in the importance of proper disposal, and cautioned against any reuse of needles and syringes. Counsel patients and parents that they should never share an OMNITROPE Pen with another person, even if the needle is changed. Sharing of the pen between patients may pose a risk of transmission of infection.

If patients are prescribed OMNITROPE Cartridge 5 mg/1.5 mL or 10 mg/1.5 mL (to be inserted into OMNITROPE Pen 5 or Pen 10 delivery systems), physicians should instruct patients to read the corresponding Instructions For Use provided with the OMNITROPE Pens delivery systems and the OMNITROPE Cartridges.

If patients are prescribed OMNITROPE for injection, physicians should instruct patients to read the Instructions For Use leaflets provided with the OMNITROPE for injection 5.8 mg/vial.

Manufactured by:

Sandoz Inc., Princeton, NJ 08540

US License No. 2003

PATIENT INFORMATION

INSTRUCTIONS FOR USE

OMNITROPE® PEN 5

OMNITROPE (om-KNEE-trope)

(somatropin) injection, for subcutaneous use

5 mg/1.5 mL Single-Patient-Use cartridges for use with

Omnitrope Pen 5

Read this Instructions for Use before you start using Omnitrope Pen 5 and each time you get a refill. There may be new information. This information does not take the place of talking to the healthcare provider about the medical condition or the treatment.

Note:

- Omnitrope is for use under the skin only (subcutaneous).
- Do not share your Omnitrope Pen or needles with anyone else. You may give an infection to them or get an infection from them.
- The “Start use by no later than” date, printed in year, month, and day on the outer carton, shows the date after which treatment should not be started with this pen.

Omnitrope Pen 5, Single-Patient-Use cartridge containing Omnitrope, needle, alcohol swab and storage case:

Figure A

Supplies you will need to give an Omnitrope Injection. See Figure A.

- Omnitrope Pen 5
- 5 mg/1.5 mL cartridge containing Omnitrope
- 1 new BD™ Pen needle (29G x 12.7 mm or 31G x 8 mm or 31G x 5 mm). Needles are not included with the Pen.
- 1 alcohol swab
- flat surface like a table
- a sharps disposal container. See Step 6 for information on how to throw away (dispose of) used needles and cartridges.

Steps you should follow to give an Omnitrope injection:

Step 1. Placing the cartridge in the Omnitrope Pen 5

Step 2. Attaching the needle to the Omnitrope Pen 5

Step 3. Priming a new cartridge

Step 4. Selecting the correct dose of Omnitrope

Step 5. Selecting the injection site and injecting the dose of Omnitrope

Step 6. Removing and throwing away the needle and empty cartridge

Step 1. Placing the cartridge in the Omnitrope Pen 5

- Take an Omnitrope cartridge out of the refrigerator and leave at room temperature for about 30 minutes. Wash and dry your hands while you wait.
- Assemble all of the supplies needed on a flat surface. Remove the Pen and cartridge from their cartons if you are preparing the injection for the first time.
- Hold the body of the Pen with 1 hand and pull off the Pen cap with the other hand. See Figure B.

Figure B

- Hold the body of the Pen with 1 hand and unscrew the cartridge holder in a clockwise direction until the Pen and cartridge holder are completely separated. See Figure C.

Figure C

- Hold the cartridge in 1 hand with the metal cap end pointing down. Insert the cartridge into the cartridge holder. See Figure D.

Figure D

- Lower the Pen body onto the cartridge holder so that the black rod presses against the cartridge plunger. Screw the cartridge holder onto the Pen body in a counterclockwise direction until the cartridge holder will not turn anymore. One of the blue arrows on the cartridge holder must line up with the yellow line mark on the Pen body. Do not over tighten the cartridge holder. See Figure E.

Figure E

Step 2. Attaching the needle to the Omnitrope Pen 5

- Take a new disposable needle and tear off the paper tab. Do not touch the needle or lay it on a surface. See Figure F.

Figure F

- Holding the cartridge holder with 1 hand, firmly press the needle onto the cartridge holder end of the Pen. See Figure G. Screw the threaded part of the needle onto the cartridge holder in a counterclockwise direction until the needle will not turn anymore. See Figure H.

Figure G
Figure H

- Gently pull off the outer needle shield and put it on a flat surface. You will use the outer needle shield later to remove the needle from the Pen after the injection is finished. See Figure I.

Figure I

Note: Check that the cartridge holder is attached to the Pen body before each injection. One of the blue arrows on the cartridge should be lined up with the yellow mark on the Pen body. After you attach the needle, you may see a few drops of medicine at the tip of the needle.

Step 3. Priming a new cartridge

- Priming is not needed for a cartridge you have used before. If the cartridge has already been primed, go to Step 4.
- Before you use a new cartridge you must first prepare it for use. Hold the Pen with the needle pointing upwards. Gently tap the cartridge holder with your finger to help air bubbles rise to the top of the cartridge. See Figure J.

Figure J

- Hold the pen with the needle pointing up and the dose window facing you and you will see the numbers in the dose window at the bottom of the Pen body. Using the dose knob on the bottom of the Pen, slowly turn the dose knob in a clockwise direction as shown in Figure K until you hear 1 “click”. The arrow on the Pen body will then be lined up with the small line between “0” and “0.1” (0.05 mg). See Figure K.

Figure K

- Remove the inner needle shield. See Figure L.
- With the needle pointing up, firmly turn the dose knob in a counterclockwise direction and back to the “0” position.

Figure L

At least 2 drops of medicine must flow out of the needle for the Pen to be properly primed. See Figure M.

Figure M

- If at least 2 drops of medicine do not flow out, set the dose to 0.05 mg and repeat this step until at least 2 drops of medicine appear at the tip of the needle.
- When you see 2 drops of medicine flow out of the needle, the Pen is correctly primed and ready to use.

Step 4. Selecting the correct dose of Omnitrope

- Hold the pen with the needle pointing up and the dose window facing you and turn (dial) the dose knob in a clockwise direction until you see the number of mg for the prescribed dose in the middle of the dose window. The dose should be lined up with the arrow on the Pen body. You will hear 1 click for every single unit you dial. See Figure N.

Do not count the clicks to measure the correct dose of medicine.

Figure N

- If you turn the dose knob past the correct dose, do not dial counterclockwise.

Instead, hold the Pen body with the needle pointing up and turn the dose knob in a clockwise direction until you see a bent arrow () in the dose dialing window. See Figure O. Now continue to turn the dose knob in a clockwise direction until you hear a click and the entire Pen body is fully extended.

The injection button can now be fully pressed, resetting the dial to “0” without giving medicine. The correct dose can now be redialed.

Figure O

- Check that the cartridge holder is still attached to the Pen body, with the blue arrow lined up with the yellow mark on the Pen body.

Step 5. Selecting the injection site and injecting the dose of Omnitrope

The best sites for injection are tissues with a layer of fat between skin and muscle such as the upper leg (thigh), buttocks, or stomach area (abdomen) as in the picture shown below. Do not inject near your belly button (navel) or waistline.

Change the injection site every day. See Figure P.

Figure P

- Select the injection site and wipe the skin with an alcohol swab as your healthcare provider showed you.
- With 1 hand, pinch a fold of loose skin at the injection site.
- With your other hand, insert the needle under the skin (at an angle of 45° to 90°) as your healthcare provider showed you. See Figure Q.

Figure Q

- After inserting the needle into the skin, push the injection button as far in as it will go and press the button firmly. A clicking sound will be heard while the dose is being injected. Continue to press firmly on the injection button for 5 seconds before you remove the needle from the skin. See Figure R.

Figure R

- Stop pressing the injection button before you carefully remove the needle from the skin.
- If the injection button cannot be pushed in completely or stops during the injection, and the cartridge is empty, then the full dose has not been given. The dose indicator window will show the amount of medicine still needed. Reset the dose knob to “0” as described in Step 4. Remove the needle as described in Step 6. Replace the empty cartridge with a new cartridge as described in Step 1. Prime the new cartridge as described in Step 3. Set the dose, which you noted, and inject. This completes your dose.

Step 6. Removing and throwing away the needle and empty cartridge

- Carefully replace the outer needle shield. See Figure S.

Figure S

- Hold the Pen by the cartridge holder and carefully remove the needle from the Pen by turning the needle in a clockwise direction. See Figure T. Recap the pen.

Figure T

- Put your used needles and cartridges in a FDA-cleared sharps disposal container right away after use. Do not throw away (dispose of) loose needles and cartridges in your household trash.
- If you do not have a FDA-cleared sharps disposal container, you may use a household container that is:
  - made of a heavy-duty plastic,
  - can be closed with a tight-fitting, puncture-resistant lid, without sharps being able to come out,
  - upright and stable during use,
  - leak-resistant, and
  - properly labeled to warn of hazardous waste inside the container.
- When your sharps disposal container is almost full, you will need to follow your community guidelines for the right way to dispose of your sharps disposal container. There may be state or local laws about how you should throw away used needles and cartridges. For more information about safe sharps disposal, and for specific information about sharps disposal in the state that you live in, go to the FDA’s website at: http://www.fda.gov/safesharpsdisposal.
- Do not dispose of your used sharps disposal container in your household trash unless your community guidelines permit this. Do not recycle your used sharps disposal container.

How should I store Omnitrope Pen 5?

- Store Omnitrope cartridges in the refrigerator between 36°F and 46°F (2°C and 8°C).
- When the Omnitrope Pen 5 contains a cartridge, do not remove the cartridge from the Pen in between injections. Store the Pen containing the cartridge in the storage case provided and place in the refrigerator.
- When the Pen does not contain a cartridge, you may store the Pen at room temperature.
- Do not freeze Omnitrope cartridges.
- Protect the Omnitrope Pen 5 and cartridge from light by storing in their cartons or the storage case.
- The Omnitrope cartridge must be thrown away 28 days after the first injection. The Omnitrope Pen 5 can be reloaded with a new cartridge and can be used multiple times.

Important information about possible problems you may have with the Omnitrope Pen 5

Problem | Possible cause | How to fix
Dial unit does not turn easily. | Dust or dirt | Turn the dial beyond the highest setting on the scale. Wipe all exposed surfaces with a clean, damp cloth.
The injection button cannot be pushed or stops during injection. The dose knob does not return to “0”. | Cartridge is empty and full dose has not been given. | Remove the needle as described in Step 6. Replace the empty cartridge with a new cartridge as described in Step 1. Prime the new cartridge as described in Step 3.
The injection button cannot be pushed or stops during injection. The dose knob does not return to “0”. | Clogged needle. | Remove the needle as described in Step 6. Replace with a new needle as described in Step 2.
No clicking is heard during the injection and dose knob moves freely. | Pen is in dose correction mode. | Remove the needle from skin. Press injection button all the way in so the dial returns to zero and repeat Step 2, Step 4 and Step 5 to give the injection.
Medicine continues to drip from the needle before injection. | Cartridge holder is not properly attached to the Pen body. | Line up blue arrow on cartridge holder with yellow mark on Pen body.
Medicine continues to drip from the needle after injection. | Needle was removed from the skin too early. | Hold the needle in the skin for 5 seconds to complete the injection, before you carefully remove the needle from the skin.; For the next injection, make sure that you hold the needle in the skin for 5 seconds.
Medicine continues to drip from the needle after injection. | Cartridge holder is not properly attached to the Pen body. | Line up blue arrow on cartridge holder with yellow mark on Pen body.
Medicine continues to drip from the needle after injection. | The needle is left on the Pen after injection. | Carefully remove the needle from the Pen right after the injection.

If the Omnitrope Pen 5 is damaged or does not work, call the pharmacy where you got the Omnitrope Pen 5. If you got your Omnitrope Pen 5 from OmniSource, call 1-877-456-6794.

For other questions or additional information, call OmniSource at 1-877-456-6794. Do not try to repair the Pen yourself.

Your Omnitrope Pen 5 is covered by a 2 year guarantee. Contact your Omnitrope Pen 5 provider after you have used the pen for 2 years to have it replaced by a new one.

This guarantee is invalid if your Omnitrope Pen 5 has not been used in accordance with the manufacturer’s instruction leaflet or if the defect has been caused by neglect, misuse or accident.

BD and BD Logo are trademarks of Becton, Dickinson and Company © 2019 BD. All rights reserved.

Manufactured by:

Sandoz Inc.

Princeton, NJ 08540

US License No. 2003

This Instructions for Use has been approved by the U.S. Food and Drug Administration.

November 2024

INSTRUCTIONS FOR USE

OMNITROPE® PEN 10

OMNITROPE (om-KNEE-trope)

(somatropin) injection, for subcutaneous use

10 mg/1.5 mL Single-Patient-Use cartridges for use with

Omnitrope Pen 10

Read this Instructions for Use before you start using Omnitrope Pen 10 and each time you get a refill. There may be new information. This information does not take the place of talking to the healthcare provider about the medical condition or the treatment.

Note:

- Omnitrope is for use under the skin only (subcutaneous).
- Do not share your Omnitrope Pen or needles with anyone else. You may give an infection to them or get an infection from them.
- The “Start use by no later than” date, printed in year, month, and day on the outer carton, shows the date after which treatment should not be started with this pen.

Omnitrope Pen 10, Single-Patient-Use cartridge containing Omnitrope, needle, alcohol swab and storage case:

Figure A

Supplies you will need to give an Omnitrope Injection. See Figure A.

- Omnitrope Pen 10
- 10 mg/1.5 mL cartridge containing Omnitrope
- 1 new BD™ Pen needle (29G x 12.7 mm or 31G x 8 mm or 31G x 5 mm). Needles are not included with the Pen.
- 1 alcohol swab
- flat surface like a table
- a sharps disposal container. See Step 6 for information on how to throw away (dispose of) used needles and cartridges.

Steps you should follow to give an Omnitrope injection:

Step 1. Placing the cartridge in the Omnitrope Pen 10

Step 2. Attaching the needle to the Omnitrope Pen 10

Step 3. Priming a new cartridge

Step 4. Selecting the correct dose of Omnitrope

Step 5. Selecting the injection site and injecting the dose of Omnitrope

Step 6. Removing and throwing away the needle and empty cartridge

Step 1. Placing the cartridge in the Omnitrope Pen 10

- Take an Omnitrope cartridge out of the refrigerator and leave at room temperature for about 30 minutes. Wash and dry your hands while you wait.
- Assemble all of the supplies needed on a flat surface. Remove the Pen and cartridge from their cartons if you are preparing the injection for the first time.
- Hold the body of the Pen with 1 hand and pull off the Pen cap with the other hand. See Figure B.

Figure B

- Hold the body of the Pen with 1 hand and unscrew the cartridge holder in a clockwise direction until the Pen and cartridge holder are completely separated. See Figure C.

Figure C

- Hold the cartridge in 1 hand with the metal cap end pointing down. Insert the cartridge into the cartridge holder. See Figure D.

Figure D

- Lower the Pen body onto the cartridge holder so that the black rod presses against the cartridge plunger. Screw the cartridge holder onto the Pen body in a counterclockwise direction until the cartridge holder will not turn anymore. One of the blue arrows on the cartridge holder must line up with the white line mark on the Pen body. Do not over tighten the cartridge holder. See Figure E.

Figure E

Step 2. Attaching the needle to the Omnitrope Pen 10

- Take a new disposable needle and tear off the paper tab. Do not touch the needle or lay it on a surface. See Figure F.

Figure F

- Holding the cartridge holder with 1 hand, firmly press the needle onto the cartridge holder end of the Pen. See Figure G. Screw the threaded part of the needle onto the cartridge holder in a counterclockwise direction until the needle will not turn anymore. See Figure H.

Figure G
Figure H

- Gently pull off the outer needle shield and put it on a flat surface. You will use the outer needle shield later to remove the needle from the Pen after the injection is finished. See Figure I.

Figure I

Note: Check that the cartridge holder is attached to the Pen body before each injection. One of the blue arrows on the cartridge should be lined up with the white mark on the Pen body. After you attach the needle, you may see a few drops of medicine at the tip of the needle.

Step 3. Priming a new cartridge

- Priming is not needed for a cartridge you have used before. If the cartridge has already been primed, go to Step 4.
- Before you use a new cartridge you must first prepare it for use. Hold the Pen with the needle pointing upwards. Gently tap the cartridge holder with your finger to help air bubbles rise to the top of the cartridge. See Figure J.

Figure J

- Hold the pen with the needle pointing up and the dose window facing you and you will see the numbers in the dose window at the bottom of the Pen body. Using the dose knob on the bottom of the Pen, slowly turn the dose knob in a clockwise direction as shown in Figure K until you hear 1 “click”. The arrow on the Pen body will then be lined up with the small line between “0” and “0.2” (0.1 mg). See Figure K.

Figure K

- Remove the inner needle shield. See Figure L.
- With the needle pointing up, firmly turn the dose knob in a counterclockwise direction and back to the “0” position.

Figure L

At least 2 drops of medicine must flow out of the needle for the Pen to be properly primed. See Figure M.

Figure M

- If at least 2 drops of medicine do not flow out, set the dose to 0.1 mg and repeat this step until at least 2 drops of medicine appear at the tip of the needle.
- When you see 2 drops of medicine flow out of the needle, the Pen is correctly primed and ready to use.

Step 4. Selecting the correct dose of Omnitrope

- Hold the pen with the needle pointing up and the dose window facing you and turn (dial) the dose knob in a clockwise direction until you see the number of mg for the prescribed dose in the middle of the dose window. The dose should be lined up with the arrow on the Pen body. You will hear 1 click for every single unit you dial. See Figure N.

Do not count the clicks to measure the correct dose of medicine.

Figure N

- If you turn the dose knob past the correct dose, do not dial counterclockwise.

Instead, hold the Pen body with the needle pointing up and turn the dose knob in a clockwise direction until you see a bent arrow () in the dose dialing window. See Figure O. Now continue to turn the dose knob in a clockwise direction until you hear a click and the entire Pen body is fully extended.

The injection button can now be fully pressed, resetting the dial to “0” without giving medicine. The correct dose can now be redialed.

Figure O

- Check that the cartridge holder is still attached to the Pen body, with the blue arrow lined up with the white mark on the Pen body.

Step 5. Selecting the injection site and injecting the dose of Omnitrope

The best sites for injection are tissues with a layer of fat between skin and muscle such as the upper leg (thigh), buttocks, or stomach area (abdomen) as in the picture shown below. Do not inject near your belly button (navel) or waistline.

Change the injection site every day. See Figure P.

Figure P

- Select the injection site and wipe the skin with an alcohol swab as your healthcare provider showed you.
- With 1 hand, pinch a fold of loose skin at the injection site.
- With your other hand, insert the needle under the skin (at an angle of 45° to 90°) as your healthcare provider showed you. See Figure Q.

Figure Q

- After inserting the needle into the skin, push the injection button as far in as it will go and press the button firmly. A clicking sound will be heard while the dose is being injected. Continue to press firmly on the injection button for 5 seconds before you remove the needle from the skin. See Figure R.

Figure R

- Stop pressing the injection button before you carefully remove the needle from the skin.
- If the injection button cannot be pushed in completely or stops during the injection, and the cartridge is empty, then the full dose has not been given. The dose indicator window will show the amount of medicine still needed. Reset the dose knob to “0” as described in Step 4. Remove the needle as described in Step 6. Replace the empty cartridge with a new cartridge as described in Step 1. Prime the new cartridge as described in Step 3. Set the dose, which you noted, and inject. This completes your dose.

Step 6. Removing and throwing away the needle and empty cartridge

- Carefully replace the outer needle shield. See Figure S.

Figure S

- Hold the Pen by the cartridge holder and carefully remove the needle from the Pen by turning the needle in a clockwise direction. See Figure T. Recap the pen.

Figure T

- Put your used needles and cartridges in a FDA-cleared sharps disposal container right away after use. Do not throw away (dispose of) loose needles and cartridges in your household trash.
- If you do not have a FDA-cleared sharps disposal container, you may use a household container that is:
  - made of a heavy-duty plastic,
  - can be closed with a tight-fitting, puncture-resistant lid, without sharps being able to come out,
  - upright and stable during use,
  - leak-resistant, and
  - properly labeled to warn of hazardous waste inside the container.
- When your sharps disposal container is almost full, you will need to follow your community guidelines for the right way to dispose of your sharps disposal container. There may be state or local laws about how you should throw away used needles and cartridges. For more information about safe sharps disposal, and for specific information about sharps disposal in the state that you live in, go to the FDA’s website at: http://www.fda.gov/safesharpsdisposal.
- Do not dispose of your used sharps disposal container in your household trash unless your community guidelines permit this. Do not recycle your used sharps disposal container.

How should I store Omnitrope Pen 10?

- Store Omnitrope cartridges in the refrigerator between 36°F and 46°F (2°C and 8°C).
- When the Omnitrope Pen 10 contains a cartridge, do not remove the cartridge from the Pen in between injections. Store the Pen containing the cartridge in the storage case provided and place in the refrigerator.
- When the Pen does not contain a cartridge, you may store the Pen at room temperature.
- Do not freeze Omnitrope cartridges.
- Protect the Omnitrope Pen 10 and cartridge from light by storing in their cartons or the storage case.
- The Omnitrope cartridge must be thrown away 28 days after the first injection. The Omnitrope Pen 10 can be reloaded with a new cartridge and can be used multiple times.

Important information about possible problems you may have with the Omnitrope Pen 10

Problem | Possible cause | How to fix
Dial unit does not turn easily. | Dust or dirt | Turn the dial beyond the highest setting on the scale. Wipe all exposed surfaces with a clean, damp cloth.
The injection button cannot be pushed or stops during injection. The dose knob does not return to “0”. | Cartridge is empty and full dose has not been given. | Remove the needle as described in Step 6. Replace the empty cartridge with a new cartridge as described in Step 1. Prime the new cartridge as described in Step 3.
The injection button cannot be pushed or stops during injection. The dose knob does not return to “0”. | Clogged needle. | Remove the needle as described in Step 6. Replace with a new needle as described in Step 2.
No clicking is heard during the injection and dose knob moves freely. | Pen is in dose correction mode. | Remove the needle from skin. Press injection button all the way in so the dial returns to zero and repeat Step 2, Step 4 and Step 5 to give the injection.
Medicine continues to drip from the needle before injection. | Cartridge holder is not properly attached to the Pen body. | Line up blue arrow on cartridge holder with white mark on Pen body.
Medicine continues to drip from the needle after injection. | Needle was removed from the skin too early. | Hold the needle in the skin for 5 seconds to complete the injection, before you carefully remove the needle from the skin.; For the next injection, make sure that you hold the needle in the skin for 5 seconds.
Medicine continues to drip from the needle after injection. | Cartridge holder is not properly attached to the Pen body. | Line up blue arrow on cartridge holder with white mark on Pen body.
Medicine continues to drip from the needle after injection. | The needle is left on the Pen after injection. | Carefully remove the needle from the Pen right after the injection.

If the Omnitrope Pen 10 is damaged or does not work, call the pharmacy where you got the Omnitrope Pen 10. If you got your Omnitrope Pen 10 from OmniSource, call 1-877-456-6794.

For other questions or additional information, call OmniSource at 1-877-456-6794. Do not try to repair the Pen yourself.

Your Omnitrope Pen 10 is covered by a 2 year guarantee. Contact your Omnitrope Pen 10 provider after you have used the pen for 2 years to have it replaced by a new one.

This guarantee is invalid if your Omnitrope Pen 10 has not been used in accordance with the manufacturer’s instruction leaflet or if the defect has been caused by neglect, misuse or accident.

BD and BD Logo are trademarks of Becton, Dickinson and Company © 2019 BD. All rights reserved.

Manufactured by:

Sandoz Inc.

Princeton, NJ 08540

US License No. 2003

This Instructions for Use has been approved by the U.S. Food and Drug Administration.

November 2024

INSTRUCTIONS FOR USE

OMNITROPE (om-KNEE-trope)

(somatropin) for injection, for subcutaneous use

OMNITROPE® 5.8 mg/vial

The following instructions explain how to inject OMNITROPE 5.8 mg. Do not inject OMNITROPE yourself until your healthcare provider has taught you and you understand the instructions. Ask your healthcare provider or pharmacist if you have any questions about injecting OMNITROPE.

- OMNITROPE 5.8 mg is for Single-Patient-Use.
- The concentration of OMNITROPE after mixing is 5 mg/mL.
- After mixing, OMNITROPE 5.8 mg contains a preservative and should not be used in newborns.

Preparation

Collect the needed items before you begin:

- a vial with OMNITROPE 5.8 mg
- a vial with diluent (mixing liquid - Bacteriostatic Water for Injection containing benzyl alcohol as preservative) for OMNITROPE 5.8 mg
- a sterile, disposable 3 mL syringe and needle for withdrawing the diluent from the vial (not supplied in the pack)
- sterile disposable 1 mL syringes and needles for under the skin (subcutaneous) injection (not supplied in the pack)
- 2 alcohol swabs (not supplied in the pack)

Wash your hands before you start with the next steps.

Mixing OMNITROPE 5.8 mg

- Remove the protective caps from the two vials. With one alcohol swab, clean both the rubber top of the vial that contains the powder and the rubber top of the vial that contains diluent.

- Next use the sterile diluent vial, the disposal 3 mL syringe and a needle.
- Attach the needle to the syringe (if not attached already). Pull back the syringe plunger and fill the syringe with air. Push the needle fitted to the syringe through the rubber top of the diluent vial, push all the air from the syringe into the vial, turn the vial upside down, and withdraw all the diluent from the vial into the syringe. Remove the syringe and needle.

- Next take the syringe with the diluent in it and push the needle through the rubber stopper of the vial that contains the white powder. Inject the diluent slowly. Aim the stream of liquid against the glass wall in order to avoid foam. Remove the syringe and needle and throw them away.

- Gently swirl the vial until the content is completely dissolved. Do not shake.

- If the medicine is cloudy or contains particles, it should not be used. The medicine must be clear and colorless after mixing.
- After mixing the medicine, the medicine in the vial must be used within 3 weeks. Store the vial in a refrigerator between 36°F to 46°F (2°C to 8°C) after mixing and using it each time.

Measuring the Dose of OMNITROPE 5.8 mg to Be Injected

- Next use the sterile, disposable 1 mL (or similar) syringe and needle for subcutaneous injection. Push the needle through the rubber top of the vial that contains the medicine that you have just mixed.
- Turn the vial and the syringe upside down.

- Be sure the tip of the syringe is in the OMNITROPE mixed medicine.
- Pull back on the plunger slowly and withdraw the dose prescribed by your healthcare provider into the syringe.
- Hold the syringe with the needle in the vial pointing up and remove the syringe from the vial.
- Check for air bubbles in the syringe. If you see any bubbles, pull the plunger slightly back; tap the syringe gently, with the needle pointing upwards, until the bubble disappears. Push the plunger slowly back up to the correct dose. If there is not enough medicine in the syringe after removing the air bubbles, draw more medicine into the syringe from the mixed medicine vial and repeat checking for bubbles.
- Look at the mixed medicine in the syringe before using. Do not use if discolored or particles are present. You are now ready to inject the dose.

Injecting OMNITROPE 5.8 mg

- Choose the site of injection on your body. The best sites for injection are tissues with a layer of fat between skin and muscle such as the upper leg (thigh), buttocks, or stomach area (abdomen) as in the picture shown below. Do not inject near your belly button (navel) or waistline.

- Make sure you rotate the injection sites on your body. Inject at least 1/2 inch from the last injection. Change the places on your body where you inject, as instructed by your healthcare provider.
- Before you make an injection, clean your skin well with an alcohol swab. Wait for the area to air dry.

- With one hand, pinch a fold of loose skin at the injection site. With your other hand, hold the syringe as you would hold a pencil. Insert the needle into the pinched skin straight in or at a slight angle (an angle of 45° to 90°). After the needle is in, remove the hand used to pinch the skin and use it to hold the syringe barrel. Pull back the plunger very slightly with one hand. If blood comes into the syringe, the needle has entered a blood vessel. Do not inject into this site; withdraw the needle and repeat the procedure at a different site. If no blood comes into the syringe, inject the solution by pushing the plunger all the way down gently.

- Pull the needle straight out of the skin. After injection, press the injection site with a small bandage or sterile gauze if needed for bleeding, for several seconds. Do not massage or rub the injection site.

After Injecting OMNITROPE 5.8 mg

- Put your used needles and syringes in a FDA-cleared sharps disposal container right away after use. Do not throw away (dispose of) loose needles and syringes in your household trash.
- If you do not have a FDA-cleared sharps disposal container, you may use a household container that is:
  - made of a heavy-duty plastic,
  - can be closed with a tight-fitting, puncture-resistant lid, without sharps being able to come out,
  - upright and stable during use,
  - leak-resistant, and
  - properly labeled to warn of hazardous waste inside the container.
- When your sharps disposal container is almost full, you will need to follow your community guidelines for the right way to dispose of your sharps disposal container. There may be state or local laws about how you should throw away used needles and cartridges. For more information about safe sharps disposal, and for specific information about sharps disposal in the state that you live in, go to the FDA’s website at: http://www.fda.gov/safesharpsdisposal.
- Do not dispose of your used sharps disposal container in your household trash unless your community guidelines permit this. Do not recycle your used sharps disposal container.

How should I store OMNITROPE 5.8 mg?

- Before Use: store the vials in the refrigerator between 36°F to 46°F (2°C to 8°C) until the expiration date. Do not use if the expiration date has passed.
- After Mixing: store the vial of mixed medicine in the refrigerator between 36°F to 46°F (2°C to 8°C) and use within 3 weeks. Throw away any unused medicine after 3 weeks.
- Protect the vials from light by storing in their cartons.
- Do not freeze.
- The liquid should be clear after removal from the refrigerator. If the liquid is cloudy or contains particles, throw away the vial. Do not inject the medicine from this vial. Start over with a new vial of OMNITROPE 5.8 mg. Call your pharmacist if you need a replacement.
- Before each use clean the rubber top of the mixed medicine vial with an alcohol swab. You must use a new disposable 1 mL syringe and needle for each injection.

Manufactured by:

Sandoz Inc.

Princeton, NJ 08540

US License No. 2003

This Instructions for Use has been approved by the U.S. Food and Drug Administration.

November 2024

5 mg/1.5 mL Carton

NDC 0781-3001-07

Omnitrope®

Somatropin

injection

5 mg/1.5 mL

For subcutaneous injection only

Rx only

Each Single-Patient-Use Cartridge contains somatropin 5 mg/1.5 mL

1 cartridge

SANDOZ

10 mg/1.5 mL Carton

NDC 0781-3004-07

Omnitrope®

Somatropin

injection

10 mg/1.5 mL

For subcutaneous injection only

Rx only

Each Single-Patient-Use Cartridge contains somatropin 10 mg/1.5 mL

1 cartridge

SANDOZ

5.8 mg Carton

NDC 0781-4004-36

Omnitrope®

(somatropin) for injection

and

diluent with preservative (Bacteriostatic Water for Injection 1.14 mL)

5.8 mg/vial

Each carton contains:

8 Single-Patient-Use Vials of Omnitrope 5.8 mg/vial

8 Single-Dose Vials of Bacteriostatic water for injection 1.14 mL

For subcutaneous injection only

Rx only

NOT FOR USE IN NEWBORNS

SANDOZ